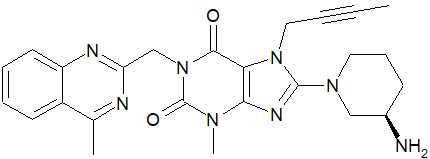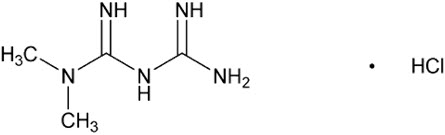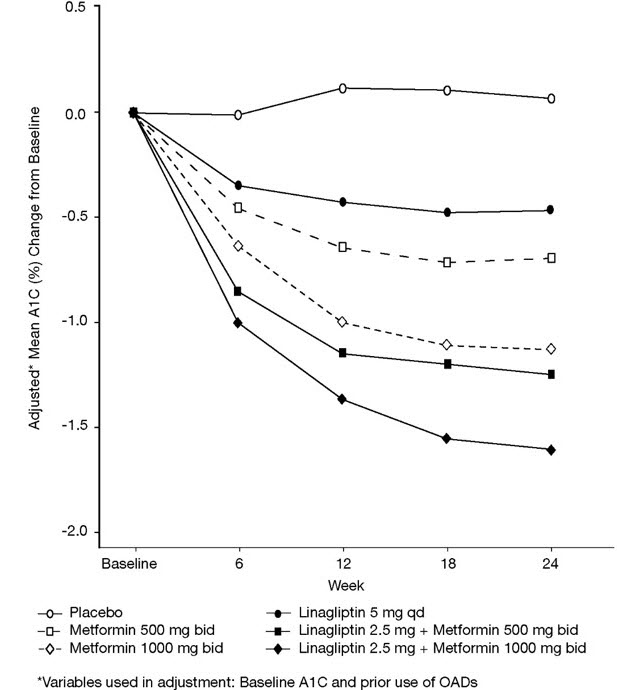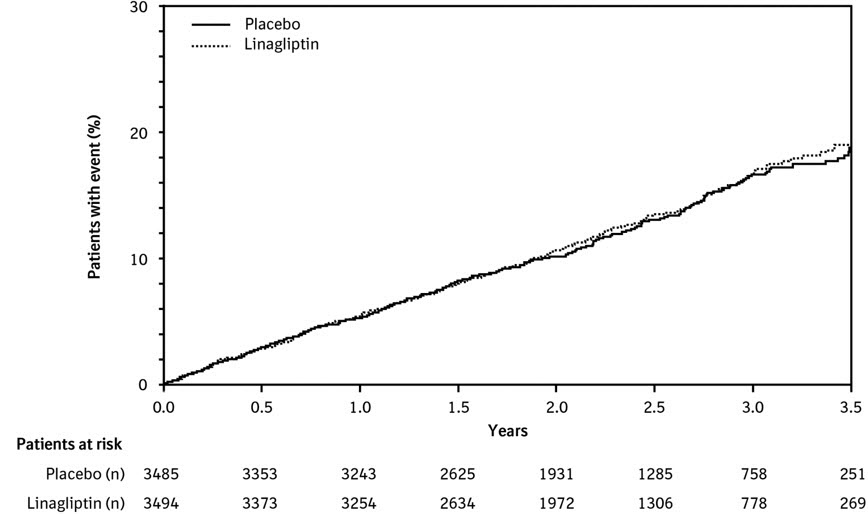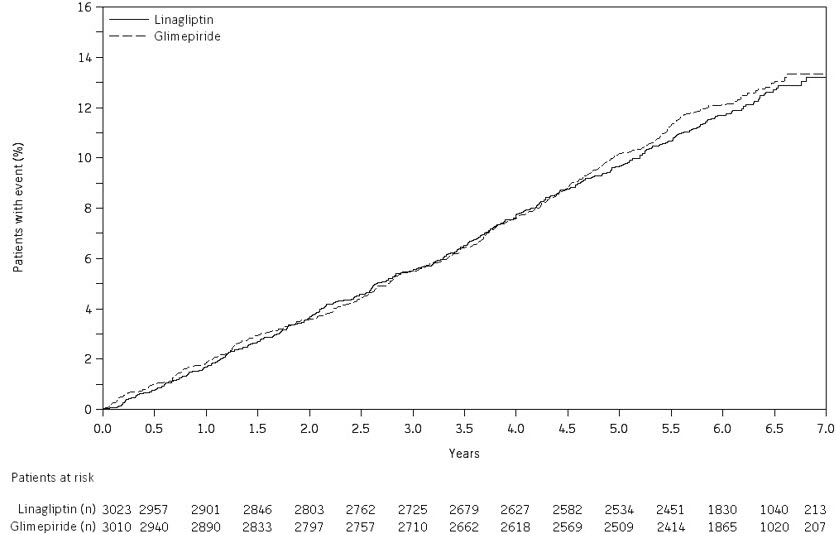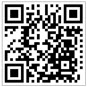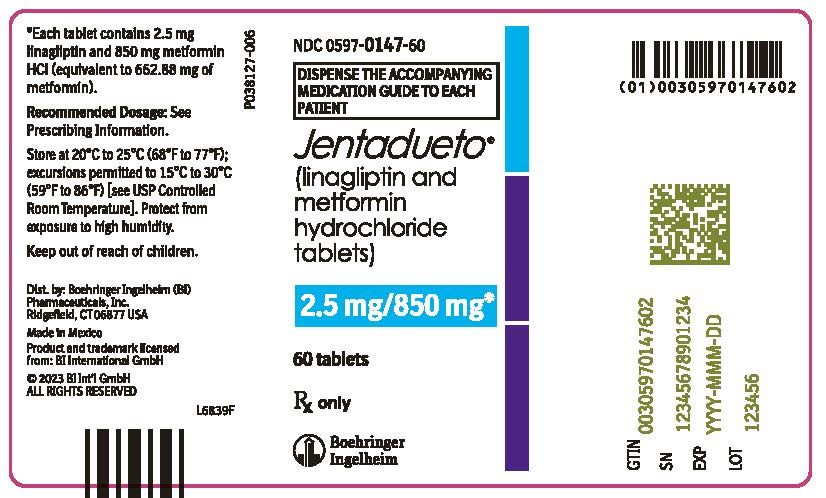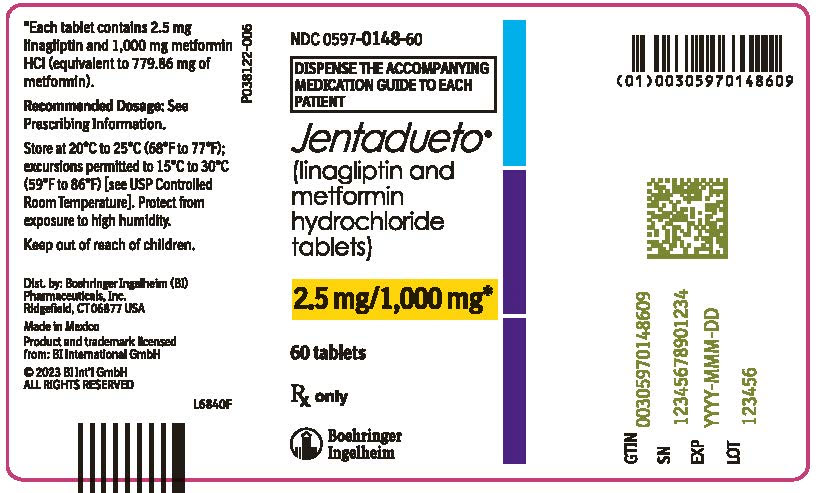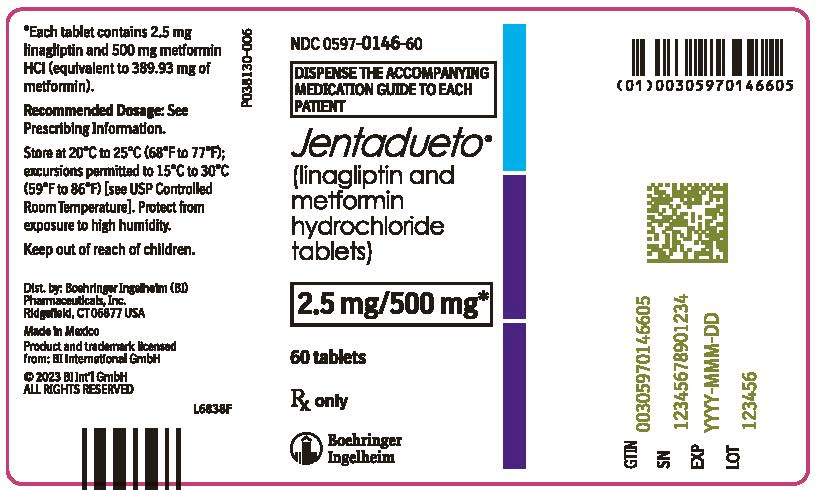 DRUG LABEL: Jentadueto
NDC: 0597-0147 | Form: TABLET, FILM COATED
Manufacturer: Boehringer Ingelheim Pharmaceuticals, Inc.
Category: prescription | Type: HUMAN PRESCRIPTION DRUG LABEL
Date: 20240627

ACTIVE INGREDIENTS: LINAGLIPTIN 2.5 mg/1 1; METFORMIN HYDROCHLORIDE 850 mg/1 1

HIGHLIGHTS OF PRESCRIBING INFORMATION

These highlights do not include all the information needed to use JENTADUETO safely and effectively. See full prescribing information for JENTADUETO.
JENTADUETO® (linagliptin and metformin hydrochloride tablets), for oral use
Initial U.S. Approval: 2012

WARNING: LACTIC ACIDOSIS

See full prescribing information for complete boxed warning.

- Postmarketing cases of metformin-associated lactic acidosis have resulted in death, hypothermia, hypotension, and resistant bradyarrhythmias. Symptoms included malaise, myalgias, respiratory distress, somnolence, and abdominal pain. Laboratory abnormalities included elevated blood lactate levels, anion gap acidosis, increased lactate/pyruvate ratio; and metformin plasma levels generally >5 mcg/mL. (5.1)
- Risk factors include renal impairment, concomitant use of certain drugs, age ≥65 years old, radiological studies with contrast, surgery and other procedures, hypoxic states, excessive alcohol intake, and hepatic impairment. Steps to reduce the risk of and manage metformin-associated lactic acidosis in these high risk groups are provided in the Full Prescribing Information. (5.1)
- If lactic acidosis is suspected, discontinue JENTADUETO and institute general supportive measures in a hospital setting. Prompt hemodialysis is recommended. (5.1)

1 INDICATIONS AND USAGE

JENTADUETO is a combination of linagliptin, a dipeptidyl peptidase-4 (DPP-4) inhibitor and metformin hydrochloride (HCl), a biguanide, indicated as an adjunct to diet and exercise to improve glycemic control in adults with type 2 diabetes mellitus (1)

Limitations of Use

- Not recommended in patients with type 1 diabetes mellitus (1)
- Has not been studied in patients with a history of pancreatitis (1)

2 DOSAGE AND ADMINISTRATION

- Individualize the starting dosage of JENTADUETO based on the patient's current regimen (2.1)
- The maximum recommended dosage is 2.5 mg linagliptin/1,000 mg metformin HCl twice daily (2.1)
- Take orally twice daily with meals, with gradual dosage escalation to reduce the gastrointestinal effects due to metformin (2.1)
- Prior to initiation, assess renal function with estimated glomerular filtration rate (eGFR) (2.2)
  - Do not use in patients with eGFR below 30 mL/min/1.73 m^2
  - Initiation is not recommended in patients with eGFR between 30 - 45 mL/min/1.73 m^2
  - Assess risk/benefit of continuing if eGFR falls below 45 mL/min/1.73 m^2
  - Discontinue if eGFR falls below 30 mL/min/1.73 m^2
- JENTADUETO may need to be discontinued at time of, or prior to, iodinated contrast imaging procedures (2.3)

3 DOSAGE FORMS AND STRENGTHS

Tablets:
2.5 mg linagliptin/500 mg metformin HCl (3)
2.5 mg linagliptin/850 mg metformin HCl (3)
2.5 mg linagliptin/1,000 mg metformin HCl (3)

4 CONTRAINDICATIONS

- Severe renal impairment (eGFR below 30 mL/min/1.73 m^2) (4)
- Metabolic acidosis, including diabetic ketoacidosis (4)
- Hypersensitivity to linagliptin, metformin, or any of the excipients in JENTADUETO (4)

5 WARNINGS AND PRECAUTIONS

- Lactic acidosis: See boxed warning (5.1)
- Pancreatitis: There have been reports of acute pancreatitis, including fatal pancreatitis. If pancreatitis is suspected, promptly discontinue JENTADUETO. (5.2)
- Hypoglycemia: Consider lowering the dosage of insulin secretagogue or insulin to reduce the risk of hypoglycemia when initiating JENTADUETO (5.3)
- Hypersensitivity reactions: Serious hypersensitivity reactions (e.g., anaphylaxis, angioedema, and exfoliative skin conditions) have occurred with JENTADUETO. If hypersensitivity reactions occur discontinue JENTADUETO, treat promptly, and monitor until signs and symptoms resolve. (5.4)
- Vitamin B12 deficiency: Metformin may lower vitamin B12 levels. Measure hematologic parameters annually and vitamin B12 at 2 to 3 year intervals and manage any abnormalities. (5.5)
- Arthralgia: Severe and disabling arthralgia has been reported in patients taking linagliptin. Consider as a possible cause for severe joint pain and discontinue drug if appropriate. (5.6)
- Bullous pemphigoid: There have been reports of bullous pemphigoid requiring hospitalization. Tell patients to report development of blisters or erosions. If bullous pemphigoid is suspected, discontinue JENTADUETO. (5.7)
- Heart failure: Heart failure has been observed with two other members of the DPP-4 inhibitor class. Consider risks and benefits of JENTADUETO in patients who have known risk factors for heart failure. Monitor for signs and symptoms. (5.8)

6 ADVERSE REACTIONS

Most common adverse reactions (incidence ≥5% and more often than placebo) were nasopharyngitis and diarrhea (6.1)

To report SUSPECTED ADVERSE REACTIONS, contact Boehringer Ingelheim Pharmaceuticals, Inc. at 1-800-542-6257 or FDA at 1-800-FDA-1088 or www.fda.gov/medwatch.

7 DRUG INTERACTIONS

- Carbonic Anhydrase Inhibitors: May increase risk of lactic acidosis. Consider more frequent monitoring. (7)
- Drugs that Reduce Metformin Clearance: May increase risk of lactic acidosis. Consider benefits and risks of concomitant use. (7)
- Alcohol: Can potentiate the effect of metformin on lactate metabolism. Warn patients against excessive alcohol intake. (7)
- Strong P-glycoprotein/CYP3A4 Inducer: Efficacy may be reduced when administered in combination (e.g., rifampin). Use of alternative treatments is strongly recommended. (7)

8 USE IN SPECIFIC POPULATIONS

- Females and Males of Reproductive Potential: Advise premenopausal females of the potential for an unintended pregnancy (8.3)
- Geriatric Use: Assess renal function more frequently (8.5)
- Hepatic Impairment: Avoid use in patients with hepatic impairment (8.7)

FULL PRESCRIBING INFORMATION

WARNING: LACTIC ACIDOSIS

Postmarketing cases of metformin-associated lactic acidosis have resulted in death, hypothermia, hypotension, and resistant bradyarrhythmias. The onset of metformin-associated lactic acidosis is often subtle, accompanied only by nonspecific symptoms such as malaise, myalgias, respiratory distress, somnolence, and abdominal pain. Metformin-associated lactic acidosis was characterized by elevated blood lactate levels (>5 mmol/Liter), anion gap acidosis (without evidence of ketonuria or ketonemia), an increased lactate/pyruvate ratio; and metformin plasma levels generally >5 mcg/mL [see Warnings and Precautions (5.1)].

Risk factors for metformin-associated lactic acidosis include renal impairment, concomitant use of certain drugs (e.g., carbonic anhydrase inhibitors such as topiramate), age 65 years old or greater, having a radiological study with contrast, surgery and other procedures, hypoxic states (e.g., acute congestive heart failure), excessive alcohol intake, and hepatic impairment.

Steps to reduce the risk of and manage metformin-associated lactic acidosis in these high risk groups are provided in the full prescribing information [see Dosage and Administration (2.2), Contraindications (4), Warnings and Precautions (5.1), Drug Interactions (7), and Use in Specific Populations (8.6, 8.7)].

If metformin-associated lactic acidosis is suspected, immediately discontinue JENTADUETO and institute general supportive measures in a hospital setting. Prompt hemodialysis is recommended [see Warnings and Precautions (5.1)].

1 INDICATIONS AND USAGE

JENTADUETO is indicated as an adjunct to diet and exercise to improve glycemic control in adults with type 2 diabetes mellitus.

Limitations of Use

JENTADUETO is not recommended in patients with type 1 diabetes mellitus.

JENTADUETO has not been studied in patients with a history of pancreatitis. It is unknown whether patients with a history of pancreatitis are at an increased risk for the development of pancreatitis while using JENTADUETO [see Warnings and Precautions (5.2)].

2 DOSAGE AND ADMINISTRATION

2.1 Recommended Dosage and Administration

The dosage of JENTADUETO should be individualized on the basis of both effectiveness and tolerability, while not exceeding the maximum recommended dosage of 2.5 mg linagliptin/1,000 mg metformin hydrochloride (HCl), taken orally twice daily. JENTADUETO should be given twice daily with meals. Dosage escalation should be gradual to reduce the gastrointestinal (GI) side effects associated with metformin use.

Recommended starting dosage:

- In patients currently not treated with metformin HCl, initiate treatment with 2.5 mg linagliptin/500 mg metformin HCl twice daily.
- In patients already treated with metformin HCl, start with 2.5 mg linagliptin and the current dosage of metformin HCl taken at each of the two daily meals (e.g., a patient on metformin HCl 1,000 mg twice daily would be started on 2.5 mg linagliptin/1,000 mg metformin HCl twice daily with meals).
- Patients already treated with linagliptin and metformin HCl individual components may be switched to JENTADUETO containing the same dosages of each component.

2.2 Recommended Dosing in Renal Impairment

Assess renal function prior to initiation of JENTADUETO and periodically thereafter.

JENTADUETO is contraindicated in patients with an estimated glomerular filtration rate (eGFR) below 30 mL/min/1.73 m^2.

Initiation of JENTADUETO in patients with an eGFR between 30-45 mL/min/1.73 m^2 is not recommended.

In patients taking JENTADUETO whose eGFR later falls below 45 mL/min/1.73 m^2, assess benefit/risk of continuing therapy.

Discontinue JENTADUETO if the patient's eGFR later falls below 30 mL/min/1.73 m^2 [see Contraindications (4) and Warnings and Precautions (5.1)].

2.3 Discontinuation for Iodinated Contrast Imaging Procedures

Discontinue JENTADUETO at the time of, or prior to, an iodinated contrast imaging procedure in patients with an eGFR between 30 and 60 mL/min/1.73 m^2; in patients with a history of liver disease, alcoholism or heart failure; or in patients who will be administered intra-arterial iodinated contrast. Re-evaluate eGFR 48 hours after the imaging procedure; restart JENTADUETO if renal function is stable [see Warnings and Precautions (5.1)].

3 DOSAGE FORMS AND STRENGTHS

JENTADUETO tablets are a combination of linagliptin and metformin HCl available as:

- 2.5 mg linagliptin/500 mg metformin HCl tablets are light yellow, oval, biconvex tablets debossed with "D2/500" on one side and the Boehringer Ingelheim symbol on the other side
- 2.5 mg linagliptin/850 mg metformin HCl tablets are light orange, oval, biconvex tablets debossed with "D2/850" on one side and the Boehringer Ingelheim symbol on the other side
- 2.5 mg linagliptin/1,000 mg metformin HCl tablets are light pink, oval, biconvex tablets debossed with "D2/1000" on one side and the Boehringer Ingelheim symbol on the other side

4 CONTRAINDICATIONS

JENTADUETO is contraindicated in patients with:

- severe renal impairment (eGFR below 30 mL/min/1.73 m^2) [see Warnings and Precautions (5.1)].
- acute or chronic metabolic acidosis, including diabetic ketoacidosis [see Warnings and Precautions (5.1)].
- hypersensitivity to linagliptin, metformin, or any of the excipients in JENTADUETO, reactions such as anaphylaxis, angioedema, exfoliative skin conditions, urticaria, or bronchial hyperreactivity have occurred with linagliptin [see Warnings and Precautions (5.4) and Adverse Reactions (6.1)].

5 WARNINGS AND PRECAUTIONS

5.1 Lactic Acidosis

Metformin

There have been postmarketing cases of metformin-associated lactic acidosis, including fatal cases. These cases had a subtle onset and were accompanied by nonspecific symptoms such as malaise, myalgias, abdominal pain, respiratory distress, or increased somnolence; however, hypothermia, hypotension and resistant bradyarrhythmias have occurred with severe acidosis. Metformin-associated lactic acidosis was characterized by elevated blood lactate concentrations (>5 mmol/Liter), anion gap acidosis (without evidence of ketonuria or ketonemia), and an increased lactate:pyruvate ratio; metformin plasma levels generally >5 mcg/mL. Metformin decreases liver uptake of lactate increasing lactate blood levels which may increase risk of lactic acidosis, especially in patients at risk.

If metformin-associated lactic acidosis is suspected, general supportive measures should be instituted promptly in a hospital setting, along with immediate discontinuation of JENTADUETO. In JENTADUETO-treated patients with a diagnosis or strong suspicion of lactic acidosis, prompt hemodialysis is recommended to correct the acidosis and remove accumulated metformin (metformin is dialyzable, with clearance of up to 170 mL/min under good hemodynamic conditions). Hemodialysis has often resulted in reversal of symptoms and recovery.

Educate patients and their families about the symptoms of lactic acidosis and if these symptoms occur instruct them to discontinue JENTADUETO and report these symptoms to their healthcare provider.

For each of the known and possible risk factors for metformin-associated lactic acidosis, recommendations to reduce the risk of and manage metformin-associated lactic acidosis are provided below:

Renal Impairment: The postmarketing metformin-associated lactic acidosis cases primarily occurred in patients with significant renal impairment. The risk of metformin accumulation and metformin-associated lactic acidosis increases with the severity of renal impairment because metformin is substantially excreted by the kidney. Clinical recommendations based upon the patient's renal function include [see Dosage and Administration (2.2) and Clinical Pharmacology (12.3)]:

- Before initiating JENTADUETO, obtain an estimated glomerular filtration rate (eGFR).
- JENTADUETO is contraindicated in patients with an eGFR less than 30 mL/min/1.73 m^2 [see Contraindications (4)].
- Initiation of JENTADUETO is not recommended in patients with eGFR between 30 – 45 mL/min/1.73 m^2.
- Obtain an eGFR at least annually in all patients taking JENTADUETO. In patients at increased risk for the development of renal impairment (e.g., the elderly), renal function should be assessed more frequently.
- In patients taking JENTADUETO whose eGFR later falls below 45 mL/min/1.73 m^2, assess the benefit and risk of continuing therapy.

Drug Interactions: The concomitant use of JENTADUETO with specific drugs may increase the risk of metformin-associated lactic acidosis: those that impair renal function, result in significant hemodynamic change, interfere with acid-base balance or increase metformin accumulation [see Drug Interactions (7)]. Therefore, consider more frequent monitoring of patients.

Age 65 or Greater: The risk of metformin-associated lactic acidosis increases with the patient's age because elderly patients have a greater likelihood of having hepatic, renal, or cardiac impairment than younger patients. Assess renal function more frequently in elderly patients [see Use in Specific Populations (8.5)].

Radiological Studies with Contrast: Administration of intravascular iodinated contrast agents in metformin-treated patients has led to an acute decrease in renal function and the occurrence of lactic acidosis. Stop JENTADUETO at the time of, or prior to, an iodinated contrast imaging procedure in patients with an eGFR between 30 and 60 mL/min/1.73 m^2; in patients with a history of hepatic impairment, alcoholism, or heart failure; or in patients who will be administered intra-arterial iodinated contrast. Re-evaluate eGFR 48 hours after the imaging procedure, and restart JENTADUETO if renal function is stable.

Surgery and Other Procedures: Withholding of food and fluids during surgical or other procedures may increase the risk for volume depletion, hypotension and renal impairment. JENTADUETO should be temporarily discontinued while patients have restricted food and fluid intake.

Hypoxic States: Several of the postmarketing cases of metformin-associated lactic acidosis occurred in the setting of acute congestive heart failure (particularly when accompanied by hypoperfusion and hypoxemia). Cardiovascular collapse (shock), acute myocardial infarction, sepsis, and other conditions associated with hypoxemia have been associated with lactic acidosis and may also cause prerenal azotemia. When such events occur, discontinue JENTADUETO.

Excessive Alcohol Intake: Alcohol potentiates the effect of metformin on lactate metabolism and this may increase the risk of metformin-associated lactic acidosis. Warn patients against excessive alcohol intake while receiving JENTADUETO.

Hepatic Impairment: Patients with hepatic impairment have developed cases of metformin-associated lactic acidosis. This may be due to impaired lactate clearance resulting in higher lactate blood levels. Therefore, avoid use of JENTADUETO in patients with clinical or laboratory evidence of hepatic disease.

5.2 Pancreatitis

Acute pancreatitis, including fatal pancreatitis, has been reported in patients treated with linagliptin. In the CARMELINA trial [see Clinical Studies (14.2)], acute pancreatitis was reported in 9 (0.3%) patients treated with linagliptin and in 5 (0.1%) patients treated with placebo. Two patients treated with linagliptin in the CARMELINA trial had acute pancreatitis with a fatal outcome. There have been postmarketing reports of acute pancreatitis, including fatal pancreatitis, in patients treated with linagliptin.

Take careful notice of potential signs and symptoms of pancreatitis. If pancreatitis is suspected, promptly discontinue JENTADUETO and initiate appropriate management. It is unknown whether patients with a history of pancreatitis are at increased risk for the development of pancreatitis while using JENTADUETO.

5.3 Hypoglycemia with Concomitant Use with Insulin and Insulin Secretagogues

Insulin secretagogues and insulin are known to cause hypoglycemia. The risk of hypoglycemia is increased when JENTADUETO is used in combination with an insulin secretagogue (e.g., sulfonylurea) or insulin [see Adverse Reactions (6.1)]. Therefore, a lower dosage of the insulin secretagogue or insulin may be required to reduce the risk of hypoglycemia when used in combination with JENTADUETO.

5.4 Hypersensitivity Reactions

There have been postmarketing reports of serious hypersensitivity reactions in patients treated with linagliptin. These reactions include anaphylaxis, angioedema, and exfoliative skin conditions. Onset of these reactions occurred predominantly within the first 3 months after initiation of treatment with linagliptin, with some reports occurring after the first dose. If a serious hypersensitivity reaction is suspected, discontinue JENTADUETO, assess for other potential causes for the event, and institute alternative treatment for diabetes mellitus.

Angioedema has also been reported with other dipeptidyl peptidase-4 (DPP-4) inhibitors. Use caution in a patient with a history of angioedema to another DPP-4 inhibitor because it is unknown whether such patients will be predisposed to angioedema with JENTADUETO.

5.5 Vitamin B12 Deficiency

In metformin clinical trials of 29-week duration, a decrease to subnormal levels of previously normal serum vitamin B12 levels was observed in approximately 7% of metformin-treated patients. Such decrease, possibly due to interference with B12 absorption from the B12-intrinsic factor complex, may be associated with anemia but appears to be rapidly reversible with discontinuation of metformin or vitamin B12 supplementation. Certain individuals (those with inadequate vitamin B12 or calcium intake or absorption) appear to be predisposed to developing subnormal vitamin B12 levels. Measure hematologic parameters on an annual basis and vitamin B12 at 2 to 3 year intervals in patients on JENTADUETO and manage any abnormalities [see Adverse Reactions (6.1)].

5.6 Severe and Disabling Arthralgia

There have been postmarketing reports of severe and disabling arthralgia in patients taking linagliptin. The time to onset of symptoms following initiation of drug therapy varied from one day to years. Patients experienced relief of symptoms upon discontinuation of the medication. A subset of patients experienced a recurrence of symptoms when restarting the same drug or a different DPP-4 inhibitor. Consider DPP-4 inhibitors as a possible cause for severe joint pain and discontinue drug if appropriate.

5.7 Bullous Pemphigoid

Bullous pemphigoid was reported in 7 (0.2%) patients treated with linagliptin compared to none in patients treated with placebo in the CARMELINA trial [see Clinical Studies (14.2)], and 3 of these patients were hospitalized due to bullous pemphigoid. Postmarketing cases of bullous pemphigoid requiring hospitalization have been reported with DPP-4 inhibitor use. In reported cases, patients typically recovered with topical or systemic immunosuppressive treatment and discontinuation of the DPP-4 inhibitor. Tell patients to report development of blisters or erosions while receiving JENTADUETO. If bullous pemphigoid is suspected, JENTADUETO should be discontinued and referral to a dermatologist should be considered for diagnosis and appropriate treatment.

5.8 Heart Failure

An association between DPP-4 inhibitor treatment and heart failure has been observed in cardiovascular outcomes trials for two other members of the DPP-4 inhibitor class. These trials evaluated patients with type 2 diabetes mellitus and atherosclerotic cardiovascular disease.

Consider the risks and benefits of JENTADUETO prior to initiating treatment in patients at risk for heart failure, such as those with a prior history of heart failure and a history of renal impairment, and observe these patients for signs and symptoms of heart failure during therapy. Advise patients of the characteristic symptoms of heart failure and to immediately report such symptoms. If heart failure develops, evaluate and manage according to current standards of care and consider discontinuation of JENTADUETO.

6 ADVERSE REACTIONS

The following serious adverse reactions are described below or elsewhere in the prescribing information:

- Lactic Acidosis [see Warnings and Precautions (5.1)]
- Pancreatitis [see Warnings and Precautions (5.2)]
- Hypoglycemia with Concomitant Use with Insulin and Insulin Secretagogues [see Warnings and Precautions (5.3)]
- Hypersensitivity Reactions [see Warnings and Precautions (5.4)]
- Vitamin B12 Deficiency [see Warnings and Precautions (5.5)]
- Severe and Disabling Arthralgia [see Warnings and Precautions (5.6)]
- Bullous Pemphigoid [see Warnings and Precautions (5.7)]
- Heart Failure [see Warnings and Precautions (5.8)]

6.1 Clinical Trials Experience

Because clinical trials are conducted under widely varying conditions, adverse reaction rates observed in the clinical trials of a drug cannot be directly compared to rates in the clinical trials of another drug and may not reflect the rates observed in practice.

Linagliptin/Metformin

The safety of concomitantly administered linagliptin (daily dosage 5 mg) and metformin (mean daily dosage of approximately 1,800 mg) has been evaluated in 2,816 patients with type 2 diabetes mellitus treated for ≥12 weeks in clinical trials.

Three placebo-controlled trials with linagliptin + metformin were conducted: 2 studies were 24 weeks in duration, 1 trial was 12 weeks in duration. In the 3 placebo-controlled clinical studies, adverse reactions which occurred in ≥5% of patients receiving linagliptin + metformin (n=875) and were more common than in patients given placebo + metformin (n=539) included nasopharyngitis (5.7% vs 4.3%).

In a 24-week factorial design trial, adverse reactions reported in ≥5% of patients receiving linagliptin + metformin and were more common than in patients given placebo are shown in Table 1.

Table 1 Adverse Reactions Reported in ≥5% of Patients Treated with Linagliptin + Metformin and Greater than with Placebo in a 24-week Factorial-Design Trial
Adverse Reactions | Placebo (%) n=72 | Linagliptin Monotherapy (%) n=142 | Metformin Monotherapy (%) n=291 | Combination of Linagliptin with Metformin (%) n=286
Nasopharyngitis | 1.4 | 5.6 | 2.7 | 6.3
Diarrhea | 2.8 | 3.5 | 3.8 | 6.3

Other adverse reactions reported in clinical studies with treatment of linagliptin + metformin were hypersensitivity (e.g., urticaria, angioedema, or bronchial hyperreactivity), cough, decreased appetite, nausea, vomiting, pruritus, and pancreatitis.

Linagliptin

Adverse reactions reported in ≥2% of patients treated with linagliptin 5 mg and more commonly than in patients treated with placebo included: nasopharyngitis (7.0% vs 6.1%), diarrhea (3.3% vs 3.0%), and cough (2.1% vs 1.4%).

Rates for other adverse reactions for linagliptin 5 mg vs placebo when linagliptin was used in combination with specific anti-diabetic agents were: urinary tract infection (3.1% vs 0%) and hypertriglyceridemia (2.4% vs 0%) when linagliptin was used as add-on to sulfonylurea; hyperlipidemia (2.7% vs 0.8%) and weight increased (2.3% vs 0.8%) when linagliptin was used as add-on to pioglitazone; and constipation (2.1% vs 1%) when linagliptin was used as add-on to basal insulin therapy.

Other adverse reactions reported in clinical studies with treatment of linagliptin monotherapy were hypersensitivity (e.g., urticaria, angioedema, localized skin exfoliation, or bronchial hyperreactivity) and myalgia. In the clinical trial program, pancreatitis was reported in 15.2 cases per 10,000 patient year exposure while being treated with linagliptin compared with 3.7 cases per 10,000 patient year exposure while being treated with comparator (placebo and active comparator, sulfonylurea). Three additional cases of pancreatitis were reported following the last administered dose of linagliptin.

Metformin

The most common (>5%) adverse reactions due to initiation of metformin therapy are diarrhea, nausea/vomiting, flatulence, abdominal discomfort, indigestion, asthenia, and headache.

Other Adverse Reactions

Hypoglycemia

Linagliptin/Metformin

In a 24-week factorial design trial, hypoglycemia was reported in 4 (1.4%) of 286 subjects treated with linagliptin + metformin, 6 (2.1%) of 291 subjects treated with metformin, and 1 (1.4%) of 72 subjects treated with placebo. The incidence of hypoglycemia with plasma glucose <54 mg/dL was 8.1% in the linagliptin group (N=792) compared to 5.3% in the placebo group (N=263) when administered in combination with metformin and sulfonylurea in a 24-week trial.

Linagliptin

The incidence of severe hypoglycemia (requiring assistance) was 1.7% in the linagliptin group (N=631) compared to 1.1% in the placebo group (N=630) when administered in combination with basal insulin in a 52-week trial.

Laboratory Test Abnormalities in Clinical Trials of Linagliptin or Metformin

Linagliptin

Increase in Uric Acid: Changes in laboratory values that occurred more frequently in the linagliptin group and ≥1% more than in the placebo group were increases in uric acid (1.3% in the placebo group, 2.7% in the linagliptin group).

Increase in Lipase: In a placebo-controlled clinical trial with linagliptin in type 2 diabetes mellitus patients with micro- or macroalbuminuria, a mean increase of 30% in lipase concentrations from baseline to 24 weeks was observed in the linagliptin arm compared to a mean decrease of 2% in the placebo arm. Lipase levels above 3 times upper limit of normal were seen in 8.2% compared to 1.7% patients in the linagliptin and placebo arms, respectively.

Increase in Amylase: In a cardiovascular safety trial comparing linagliptin versus glimepiride in patients with type 2 diabetes mellitus, amylase levels above 3 times upper limit of normal were seen in 1.0% compared to 0.5% of patients in the linagliptin and glimepiride arms, respectively.

The clinical significance of elevations in lipase and amylase with linagliptin is unknown in the absence of potential signs and symptoms of pancreatitis [see Warnings and Precautions (5.2)].

Metformin

Decrease in Vitamin B12: In metformin clinical trials of 29-week duration, a decrease to subnormal levels of previously normal serum vitamin B12 levels was observed in approximately 7% of patients.

6.2 Postmarketing Experience

The following adverse reactions have been identified during postapproval use. Because these reactions are reported voluntarily from a population of uncertain size, it is generally not possible to reliably estimate their frequency or establish a causal relationship to drug exposure.

Linagliptin

- Gastrointestinal Disorders: Acute pancreatitis, including fatal pancreatitis [see Indications and Usage (1)], mouth ulceration, stomatitis
- Immune System Disorders: Hypersensitivity reactions including anaphylaxis, angioedema, and exfoliative skin conditions
- Musculoskeletal and Connective Tissue Disorders: Rhabdomyolysis, severe and disabling arthralgia
- Skin and Subcutaneous Tissue Disorders: Bullous pemphigoid, rash

Metformin

- Hepatobiliary Disorders: Cholestatic, hepatocellular, and mixed hepatocellular liver injury

7 DRUG INTERACTIONS

Table 2 describes clinically relevant interactions with JENTADUETO.

Table 2 Clinically Relevant Interactions with JENTADUETO
Carbonic Anhydrase Inhibitors
Clinical Impact | Topiramate or other carbonic anhydrase inhibitors (e.g., zonisamide, acetazolamide or dichlorphenamide) frequently cause a decrease in serum bicarbonate and induce non-anion gap, hyperchloremic metabolic acidosis. Concomitant use of these drugs with JENTADUETO may increase the risk of lactic acidosis.
Intervention | Consider more frequent monitoring of these patients.
Drugs that Reduce Metformin Clearance
Clinical Impact | Concomitant use of drugs that interfere with common renal tubular transport systems involved in the renal elimination of metformin (e.g., organic cationic transporter-2 [OCT2] / multidrug and toxin extrusion [MATE] inhibitors such as ranolazine, vandetanib, dolutegravir, and cimetidine) could increase systemic exposure to metformin and may increase the risk for lactic acidosis [see Clinical Pharmacology (12.3)].
Intervention | Consider the benefits and risks of concomitant use.
Alcohol
Clinical Impact | Alcohol is known to potentiate the effect of metformin on lactate metabolism.
Intervention | Warn patients against excessive alcohol intake while receiving JENTADUETO.
Insulin or Insulin Secretagogues
Clinical Impact | The risk of hypoglycemia is increased when JENTADUETO is used in combination with an insulin secretagogue (e.g., sulfonylurea) or insulin.
Intervention | Coadministration of JENTADUETO with an insulin secretagogue (e.g., sulfonylurea) or insulin may require lower dosages of the insulin secretagogue or insulin to reduce the risk of hypoglycemia.
Drugs Affecting Glycemic Control
Clinical Impact | Certain drugs tend to produce hyperglycemia and may lead to loss of glycemic control. These drugs include the thiazides and other diuretics, corticosteroids, phenothiazines, thyroid products, estrogens, oral contraceptives, phenytoin, nicotinic acid, sympathomimetics, calcium channel blocking drugs, and isoniazid.
Intervention | When such drugs are administered to a patient receiving JENTADUETO, the patient should be closely observed to maintain adequate glycemic control. When such drugs are withdrawn from a patient receiving JENTADUETO, the patient should be observed closely for hypoglycemia.
Inducers of P-glycoprotein or CYP3A4 Enzymes
Clinical Impact | Rifampin decreased linagliptin exposure, suggesting that the efficacy of linagliptin may be reduced when administered in combination with a strong P-gp or CYP3A4 inducer.
Intervention | Use of alternative treatments is strongly recommended when linagliptin is to be administered with a strong P-gp or CYP3A4 inducer.

8 USE IN SPECIFIC POPULATIONS

8.1 Pregnancy

Risk Summary

The limited data with JENTADUETO and linagliptin use in pregnant women are not sufficient to inform a JENTADUETO-associated or linagliptin-associated risk for major birth defects and miscarriage. Published studies with metformin use during pregnancy have not reported a clear association with metformin and major birth defect or miscarriage risk [see Data]. There are risks to the mother and fetus associated with poorly controlled diabetes in pregnancy [see Clinical Considerations].

In animal reproduction studies, no adverse developmental effects were observed when the combination of linagliptin and metformin was administered to pregnant rats during the period of organogenesis at doses similar to the maximum recommended clinical dose, based on exposure [see Data].

The estimated background risk of major birth defects is 6% to 10% in women with pre-gestational diabetes with a HbA1c >7 and has been reported to be as high as 20% to 25% in women with HbA1c >10. The estimated background risk of miscarriage for the indicated population is unknown. In the U.S. general population, the estimated background risk of major birth defects and miscarriage in clinically recognized pregnancies is 2% to 4% and 15% to 20%, respectively.

Clinical Considerations

Disease-associated maternal and/or embryo/fetal risk

Poorly controlled diabetes in pregnancy increases the maternal risk for diabetic ketoacidosis, preeclampsia, spontaneous abortions, preterm delivery, and delivery complications. Poorly controlled diabetes increases the fetal risk for major birth defects, stillbirth, and macrosomia related morbidity.

Data

Human Data

Published data from postmarketing studies have not reported a clear association with metformin and major birth defects, miscarriage, or adverse maternal or fetal outcomes when metformin was used during pregnancy. However, these studies cannot definitely establish the absence of any metformin-associated risk because of methodological limitations, including small sample size and inconsistent comparator groups.

Animal Data

Linagliptin and metformin, the components of JENTADUETO, were coadministered to pregnant Wistar Han rats during the period of organogenesis. No adverse developmental outcome was observed at doses similar to the maximum recommended clinical dose, based on exposure. At higher doses associated with maternal toxicity, the metformin component of the combination was associated with an increased incidence of fetal rib and scapula malformations at ≥9-times a 2,000 mg clinical dose, based on exposure.

Linagliptin

No adverse developmental outcome was observed when linagliptin was administered to pregnant Wistar Han rats and Himalayan rabbits during the period of organogenesis at doses up to 240 mg/kg/day and 150 mg/kg/day, respectively. These doses represent approximately 943-times (rats) and 1,943-times (rabbits) the 5 mg maximum clinical dose, based on exposure. No adverse functional, behavioral, or reproductive outcome was observed in offspring following administration of linagliptin to Wistar Han rats from gestation day 6 to lactation day 21 at a dose 49-times the maximum recommended human dose, based on exposure.

Linagliptin crosses the placenta into the fetus following oral dosing in pregnant rats and rabbits.

Metformin HCl

Metformin HCl did not cause adverse developmental effects when administered to pregnant Sprague Dawley rats and rabbits at doses up to 600 mg/kg/day during the period of organogenesis. This represents an exposure of approximately 2- and 6-times a clinical dose of 2,000 mg, based on body surface area (mg/m^2) for rats and rabbits, respectively.

8.2 Lactation

Risk Summary

There is limited information regarding the presence of JENTADUETO or its components (linagliptin or metformin) in human milk, the effects on the breastfed infant, or the effects on milk production. However, linagliptin is present in rat milk. Limited published studies report that metformin is present in human milk [see Data]. Therefore, the developmental and health benefits of breastfeeding should be considered along with the mother's clinical need for JENTADUETO and any potential adverse effects on the breastfed child from JENTADUETO or from the underlying maternal condition.

Data

Published clinical lactation studies report that metformin is present in human milk which resulted in infant doses approximately 0.11% to 1% of the maternal weight-adjusted dosage and a milk/plasma ratio ranging between 0.13 and 1. However, the studies were not designed to definitely establish the risk of use of metformin during lactation because of small sample size and limited adverse event data collected in infants.

8.3 Females and Males of Reproductive Potential

Discuss the potential for unintended pregnancy with premenopausal women as therapy with metformin may result in ovulation in some anovulatory women.

8.4 Pediatric Use

Safety and effectiveness of JENTADUETO have not been established in pediatric patients.

Effectiveness of linagliptin was not demonstrated in a 26-week randomized, double-blind, placebo-controlled trial (NCT03429543) in 157 pediatric patients aged 10 to 17 years with inadequately controlled type 2 diabetes mellitus.

8.5 Geriatric Use

Linagliptin is minimally excreted by the kidney; however, metformin is substantially excreted by the kidney [see Warnings and Precautions (5.1) and Clinical Pharmacology (12.3)].

Linagliptin

In linagliptin studies, 1,085 linagliptin-treated patients were 65 years of age and older and 131 patients were 75 years of age and older. In these linagliptin studies, no overall differences in safety or effectiveness of linagliptin were observed between geriatric patients and younger adult patients.

Metformin

Controlled clinical studies of metformin did not include sufficient numbers of elderly patients to determine whether they respond differently from younger patients. In general, dose selection for an elderly patient should be cautious, usually starting at the low end of the dosing range, reflecting the greater frequency of decreased hepatic, renal, or cardiac function, and of concomitant disease or other drug therapy and the higher risk of lactic acidosis. Assess renal function more frequently in elderly patients [see Contraindications (4), Warnings and Precautions (5.1), and Clinical Pharmacology (12.3)].

8.6 Renal Impairment

Metformin is substantially excreted by the kidney, and the risk of metformin accumulation and lactic acidosis increases with the degree of renal impairment.

JENTADUETO is contraindicated in severe renal impairment, patients with an estimated glomerular filtration rate (eGFR) below 30 mL/min/1.73 m^2 [see Dosage and Administration (2.2), Contraindications (4), Warnings and Precautions (5.1), and Clinical Pharmacology (12.3)].

In the linagliptin treatment arm of the CARMELINA trial [see Clinical Studies (14.2)], 2,200 (63%) patients had renal impairment (eGFR <60 mL/min/1.73 m^2). Approximately 20% of the population had eGFR ≥45 to <60 mL/min/1.73 m^2, 28% of the population had eGFR ≥30 to <45 mL/min/1.73 m^2 and 15% had eGFR <30 mL/min/1.73 m^2. The overall incidence of adverse reactions were generally similar between the linagliptin and placebo treatment arms.

8.7 Hepatic Impairment

Use of metformin in patients with hepatic impairment has been associated with some cases of lactic acidosis. JENTADUETO is not recommended in patients with hepatic impairment [see Warnings and Precautions (5.1)].

10 OVERDOSAGE

In the event of an overdose with JENTADUETO, consider contacting the Poison Help line (1-800-222-1222) or medical toxicologist for additional overdosage management recommendations.

Overdose of metformin HCl has occurred, including ingestion of amounts greater than 50 grams. Lactic acidosis has been reported in approximately 32% of metformin overdose cases [see Warnings and Precautions (5.1)]. Metformin is dialyzable with a clearance of up to 170 mL/min under good hemodynamic conditions. Therefore, hemodialysis may be useful for removal of accumulated drug from patients in whom metformin overdosage is suspected.

Removal of linagliptin by hemodialysis or peritoneal dialysis is unlikely.

11 DESCRIPTION

JENTADUETO tablets for oral use contain: linagliptin and metformin HCl.

Linagliptin

Linagliptin is an inhibitor of the dipeptidyl peptidase-4 (DPP-4) enzyme.

The chemical name of linagliptin is 1H-Purine-2,6-dione, 8-[(3R)-3-amino-1-piperidinyl]-7-(2-butyn-1-yl)-3,7-dihydro-3-methyl-1-[(4-methyl-2-quinazolinyl)methyl]-

The molecular formula is C25H28N8O2 and the molecular weight is 472.54 g/mol. The structural formula is:

Linagliptin is a white to yellowish, not or only slightly hygroscopic solid substance. It is very slightly soluble in water (0.9 mg/mL). Linagliptin is soluble in methanol (ca. 60 mg/mL), sparingly soluble in ethanol (ca. 10 mg/mL), very slightly soluble in isopropanol (<1 mg/mL), and very slightly soluble in acetone (ca. 1 mg/mL).

Metformin HCl

Metformin HCl (N,N-dimethylimidodicarbonimidic diamide hydrochloride) is a biguanide. Metformin HCl is a white to off-white crystalline compound with a molecular formula of C4H11N5∙HCl and a molecular weight of 165.63 g/mol. Metformin HCl is freely soluble in water and is practically insoluble in acetone, ether, and chloroform. The pKa of metformin is 12.4. The pH of a 1% aqueous solution of metformin hydrochloride is 6.68. The structural formula is:

JENTADUETO

JENTADUETO is available for oral administration as tablets containing:

- 2.5 mg linagliptin and 500 mg metformin HCl (equivalent to 389.93 mg of metformin)
- 2.5 mg linagliptin and 850 mg metformin HCl (equivalent 662.88 mg of metformin)
- 2.5 mg linagliptin and 1,000 mg metformin HCl (equivalent to 779.86 mg of metformin)

Each film-coated tablet of JENTADUETO contains the following inactive ingredients: arginine, colloidal silicon dioxide, copovidone, corn starch, hypromellose, magnesium stearate, propylene glycol, talc, titanium dioxide, red ferric oxide (2.5 mg/850 mg; 2.5 mg/1,000 mg) and/or yellow ferric oxide (2.5 mg/500 mg; 2.5 mg/850 mg).

12 CLINICAL PHARMACOLOGY

12.1 Mechanism of Action

JENTADUETO

JENTADUETO contains: linagliptin, a dipeptidyl peptidase-4 (DPP-4) inhibitor, and metformin, a biguanide.

Linagliptin

Linagliptin is an inhibitor of DPP-4, an enzyme that degrades the incretin hormones glucagon-like peptide-1 (GLP-1) and glucose-dependent insulinotropic polypeptide (GIP). Thus, linagliptin increases the concentrations of active incretin hormones, stimulating the release of insulin in a glucose-dependent manner and decreasing the levels of glucagon in the circulation. Both incretin hormones are involved in the physiological regulation of glucose homeostasis. Incretin hormones are secreted at a low basal level throughout the day and levels rise immediately after meal intake. GLP-1 and GIP increase insulin biosynthesis and secretion from pancreatic beta cells in the presence of normal and elevated blood glucose levels. Furthermore, GLP-1 also reduces glucagon secretion from pancreatic alpha cells, resulting in a reduction in hepatic glucose output.

Metformin HCl

Metformin is an antihyperglycemic agent which improves glucose tolerance in patients with type 2 diabetes mellitus, lowering both basal and postprandial plasma glucose. Metformin decreases hepatic glucose production, decreases intestinal absorption of glucose, and improves insulin sensitivity by increasing peripheral glucose uptake and utilization. With metformin therapy, insulin secretion remains unchanged while fasting insulin levels and day-long plasma insulin response may decrease.

12.2 Pharmacodynamics

Linagliptin

Linagliptin binds to DPP-4 in a reversible manner and increases the concentrations of incretin hormones. Linagliptin glucose-dependently increases insulin secretion and lowers glucagon secretion, thus resulting in a better regulation of the glucose homeostasis. Linagliptin binds selectively to DPP-4 and selectively inhibits DPP-4, but not DPP-8 or DPP-9 activity in vitro at concentrations approximating therapeutic exposures.

Cardiac Electrophysiology

In a randomized, placebo-controlled, active-comparator, 4-way crossover study, 36 healthy subjects were administered a single oral dose of linagliptin 5 mg, linagliptin 100 mg (20 times the recommended dose), moxifloxacin, and placebo. No increase in QTc was observed with either the recommended dose of 5 mg or the 100 mg dose. At the 100 mg dose, peak linagliptin plasma concentrations were approximately 38-fold higher than the peak concentrations following a 5 mg dose.

12.3 Pharmacokinetics

JENTADUETO

Administration of linagliptin 2.5 mg/metformin HCl 1,000 mg fixed-dose combination with food resulted in no change in overall exposure of linagliptin. There was no change in metformin AUC; however, mean peak serum concentration of metformin was decreased by 18% when administered with food. A delayed time-to-peak serum concentrations by 2 hours was observed for metformin under fed conditions. These changes are not likely to be clinically significant.

Absorption

Linagliptin

The absolute bioavailability of linagliptin is approximately 30%. Following oral administration, plasma concentrations of linagliptin decline in at least a biphasic manner with a long terminal half-life (>100 hours), related to the saturable binding of linagliptin to DPP-4. However, the prolonged elimination does not contribute to the accumulation of the drug. The effective half-life for accumulation of linagliptin, as determined from oral administration of multiple doses of linagliptin 5 mg, is approximately 12 hours. After once-daily dosing, steady-state plasma concentrations of linagliptin 5 mg are reached by the third dose, and Cmax and AUC increased by a factor of 1.3 at steady-state compared with the first dose. Plasma AUC of linagliptin increased in a less than dose-proportional manner in the dose range of 1 to 10 mg. The pharmacokinetics of linagliptin is similar in healthy subjects and in patients with type 2 diabetes mellitus.

Metformin HCl

The absolute bioavailability of a metformin HCl 500 mg tablet given under fasting conditions is approximately 50% to 60%. Studies using single oral doses of metformin tablets 500 mg to 1,500 mg, and 850 mg to 2,550 mg, indicate that there is a lack of dose proportionality with increasing doses, which is due to decreased absorption rather than an alteration in elimination.

Distribution

Linagliptin

The mean apparent volume of distribution at steady-state following a single intravenous dose of linagliptin 5 mg to healthy subjects is approximately 1,110 L, indicating that linagliptin extensively distributes to the tissues. Plasma protein binding of linagliptin is concentration-dependent decreasing from about 99% at 1 nmol/L to 75% to 89% at ≥30 nmol/L, reflecting saturation of binding to DPP-4 with increasing concentration of linagliptin. At high concentrations, where DPP-4 is fully saturated, 70% to 80% of linagliptin remains bound to plasma proteins and 20% to 30% is unbound in plasma. Plasma binding is not altered in patients with renal or hepatic impairment.

Metformin HCl

The apparent volume of distribution (V/F) of metformin following single oral doses of immediate-release metformin HCl tablets 850 mg averaged 654±358 L. Metformin is negligibly bound to plasma proteins. Metformin partitions into erythrocytes, most likely as a function of time.

Elimination

Linagliptin: Linagliptin has a terminal half-life of about 200 hours at steady-state, though the accumulation half-life is about 11 hours. Renal clearance at steady-state was approximately 70 mL/min.

Metformin HCl: Metformin has a plasma elimination half-life of approximately 6.2 hours. In blood, the elimination half-life is approximately 17.6 hours, suggesting that the erythrocyte mass may be a compartment of distribution.

Metabolism

Linagliptin: Following oral administration, the majority (about 90%) of linagliptin is excreted unchanged, indicating that metabolism represents a minor elimination pathway. A small fraction of absorbed linagliptin is metabolized to a pharmacologically inactive metabolite, which shows a steady-state exposure of 13.3% relative to linagliptin.

Metformin HCl: Intravenous single-dose studies in normal subjects demonstrate that metformin does not undergo hepatic metabolism (no metabolites have been identified in humans), nor biliary excretion.

Excretion

Linagliptin: Following administration of an oral [^14C] linagliptin dose to healthy subjects, approximately 85% of the administered radioactivity was eliminated via the enterohepatic system (80%) or urine (5%) within 4 days of dosing.

Metformin HCl: Following oral administration, approximately 90% of the absorbed drug is excreted via the renal route within the first 24 hours. Renal clearance is approximately 3.5 times greater than creatinine clearance, which indicates that tubular secretion is the major route of metformin elimination.

Specific Populations

Renal Impairment

JENTADUETO: Studies characterizing the pharmacokinetics of linagliptin and metformin after administration of JENTADUETO in renally impaired patients have not been performed.

Linagliptin: Under steady-state conditions, linagliptin exposure in patients with mild renal impairment was comparable to healthy subjects. In patients with moderate renal impairment under steady-state conditions, mean exposure of linagliptin increased (AUCτ,ss by 71% and Cmax by 46%) compared with healthy subjects. This increase was not associated with a prolonged accumulation half-life, terminal half-life, or an increased accumulation factor. Renal excretion of linagliptin was below 5% of the administered dose and was not affected by decreased renal function.

Patients with type 2 diabetes mellitus and severe renal impairment showed steady-state exposure approximately 40% higher than that of patients with type 2 diabetes mellitus and normal renal function (increase in AUC by 42% and Cmax by 35%). For both type 2 diabetes mellitus groups, renal excretion was below 7% of the administered dose.

These findings were further supported by the results of population pharmacokinetic analyses.

Metformin HCl: In patients with decreased renal function, the plasma and blood half-life of metformin is prolonged and the renal clearance is decreased [see Contraindications (4) and Warnings and Precautions (5.1)].

Hepatic Impairment

JENTADUETO: Studies characterizing the pharmacokinetics of linagliptin and metformin after administration of JENTADUETO in hepatically impaired patients have not been performed [see Warnings and Precautions (5.1)].

Linagliptin: In patients with mild hepatic impairment (Child-Pugh class A) steady-state exposure (AUCτ,ss) of linagliptin was approximately 25% lower and Cmax,ss was approximately 36% lower than in healthy subjects. In patients with moderate hepatic impairment (Child-Pugh class B), AUCss of linagliptin was about 14% lower and Cmax,ss was approximately 8% lower than in healthy subjects. Patients with severe hepatic impairment (Child-Pugh class C) had comparable exposure of linagliptin in terms of AUC0-24 and approximately 23% lower Cmax compared with healthy subjects. Reductions in the pharmacokinetic parameters seen in patients with hepatic impairment did not result in reductions in DPP-4 inhibition.

Metformin HCl: No pharmacokinetic studies of metformin have been conducted in patients with hepatic impairment.

Effects of Age, Body Mass Index (BMI), Gender, and Race

Linagliptin: Based on the population pharmacokinetic analysis, age, BMI, gender, and race do not have a clinically meaningful effect on pharmacokinetics of linagliptin [see Use in Specific Populations (8.5)].

Metformin HCl: Metformin pharmacokinetic parameters did not differ significantly between normal subjects and patients with type 2 diabetes mellitus when analyzed according to gender. Similarly, in controlled clinical studies in patients with type 2 diabetes mellitus, the antihyperglycemic effect of metformin was comparable in males and females.

Limited data from controlled pharmacokinetic studies of metformin in healthy elderly subjects suggest that total plasma clearance of metformin is decreased, the half-life is prolonged, and Cmax is increased, compared with healthy young subjects. From these data, it appears that the change in metformin pharmacokinetics with aging is primarily accounted for by a change in renal function.

No studies of metformin pharmacokinetic parameters according to race have been performed. In controlled clinical studies of metformin HCl in patients with type 2 diabetes mellitus, the antihyperglycemic effect was comparable in Caucasians (n=249), Blacks (n=51), and Hispanics (n=24).

Drug Interactions

Pharmacokinetic drug interaction studies with JENTADUETO have not been performed; however, such studies have been conducted with the individual components of JENTADUETO (linagliptin and metformin HCl).

Linagliptin

In vitro Assessment of Drug Interactions

Linagliptin is a weak to moderate inhibitor of CYP isozyme CYP3A4, but does not inhibit other CYP isozymes and is not an inducer of CYP isozymes, including CYP1A2, 2A6, 2B6, 2C8, 2C9, 2C19, 2D6, 2E1, and 4A11.

Linagliptin is a P-glycoprotein (P-gp) substrate, and inhibits P-gp mediated transport of digoxin at high concentrations. Based on these results and in vivo drug interaction studies, linagliptin is considered unlikely to cause interactions with other P-gp substrates at therapeutic concentrations.

In vivo Assessment of Drug Interactions

Strong inducers of CYP3A4 or P-gp (e.g., rifampin) decrease exposure to linagliptin to subtherapeutic and likely ineffective concentrations [see Drug Interactions (7)]. In vivo studies indicated evidence of a low propensity for causing drug interactions with substrates of CYP3A4, CYP2C9, CYP2C8, P-gp, and organic cationic transporter (OCT).

Table 3 describes the effect of coadministered drugs on systemic exposure of linagliptin.

Table 3 Effect of Coadministered Drugs on Systemic Exposure of Linagliptin
Coadministered Drug | Dosing of Coadministered Drug* | Dosing of Linagliptin* | Geometric Mean Ratio (ratio with/without coadministered drug) No effect=1.0
 |  |  | AUC† | Cmax
Metformin | 850 mg TID | 10 mg QD | 1.20 | 1.03
Glyburide | 1.75 mg# | 5 mg QD | 1.02 | 1.01
Pioglitazone | 45 mg QD | 10 mg QD | 1.13 | 1.07
Ritonavir | 200 mg BID | 5 mg# | 2.01 | 2.96
Rifampin** | 600 mg QD | 5 mg QD | 0.60 | 0.56
*Multiple dose (steady-state) unless otherwise noted
**For information regarding clinical recommendations [see Drug Interactions (7)].
#Single dose
†AUC = AUC(0 to 24 hours) for single-dose treatments and AUC = AUC(TAU) for multiple-dose treatments
QD=once daily
BID=twice daily
TID=three times daily

Table 4 describes the effect of linagliptin on systemic exposure of coadministered drugs.

Table 4 Effect of Linagliptin on Systemic Exposure of Coadministered Drugs
Coadministered Drug | Dosing of Coadministered Drug* | Dosing of Linagliptin* | Geometric Mean Ratio (ratio with/without coadministered drug) No effect=1.0
 |  |  |  | AUC† | Cmax
Metformin | 850 mg TID | 10 mg QD | metformin | 1.01 | 0.89
Glyburide | 1.75 mg# | 5 mg QD | glyburide | 0.86 | 0.86
Pioglitazone | 45 mg QD | 10 mg QD | pioglitazone | 0.94 | 0.86
Pioglitazone | 45 mg QD | 10 mg QD | metabolite M-III | 0.98 | 0.96
Pioglitazone | 45 mg QD | 10 mg QD | metabolite M-IV | 1.04 | 1.05
Digoxin | 0.25 mg QD | 5 mg QD | digoxin | 1.02 | 0.94
Simvastatin | 40 mg QD | 10 mg QD | simvastatin | 1.34 | 1.10
Simvastatin | 40 mg QD | 10 mg QD | simvastatin acid | 1.33 | 1.21
Warfarin | 10 mg# | 5 mg QD | R-warfarin | 0.99 | 1.00
Warfarin | 10 mg# | 5 mg QD | S-warfarin | 1.03 | 1.01
Warfarin | 10 mg# | 5 mg QD | INR | 0.93** | 1.04**
Warfarin | 10 mg# | 5 mg QD | PT | 1.03** | 1.15**
Ethinylestradiol and levonorgestrel | ethinylestradiol 0.03 mg and levonorgestrel 0.150 mg QD | 5 mg QD | ethinylestradiol | 1.01 | 1.08
Ethinylestradiol and levonorgestrel | ethinylestradiol 0.03 mg and levonorgestrel 0.150 mg QD | 5 mg QD | levonorgestrel | 1.09 | 1.13
*Multiple dose (steady-state) unless otherwise noted
#Single dose
†AUC = AUC(INF) for single-dose treatments and AUC = AUC(TAU) for multiple-dose treatments
**AUC=AUC(0-168) and Cmax=Emax for pharmacodynamic end points
INR=International Normalized Ratio
PT=Prothrombin Time
QD=once daily
TID=three times daily

Metformin HCl

Table 5 describes the effect of coadministered drugs on plasma metformin systemic exposure.

Table 5 Effect of Coadministered Drugs on Plasma Metformin Systemic Exposure
Coadministered Drug | Dosing of Coadministered Drug* | Dosing of Metformin* | Geometric Mean Ratio (ratio with/without coadministered drug) No effect=1.0
 |  |  |  | AUC† | Cmax
Glyburide | 5 mg | 850 mg | metformin | 0.91‡ | 0.93‡
Furosemide | 40 mg | 850 mg | metformin | 1.09‡ | 1.22‡
Nifedipine | 10 mg | 850 mg | metformin | 1.16 | 1.21
Propranolol | 40 mg | 850 mg | metformin | 0.90 | 0.94
Ibuprofen | 400 mg | 850 mg | metformin | 1.05‡ | 1.07‡
Cationic drugs eliminated by renal tubular secretion may reduce metformin elimination [see Drug Interactions (7)].
Cimetidine | 400 mg | 850 mg | metformin | 1.40 | 1.61
Carbonic anhydrase inhibitors may cause metabolic acidosis [see Drug Interactions (7)].
Topiramate** | 100 mg | 500 mg | metformin | 1.25 | 1.17
*All metformin and coadministered drugs were given as single doses
†AUC=AUC(INF)
‡Ratio of arithmetic means
**At steady-state with topiramate 100 mg every 12 hours and metformin 500 mg every 12 hours; AUC = AUC(0-12 hours)

Table 6 describes the effect of metformin on coadministered drug systemic exposure.

Table 6 Effect of Metformin on Coadministered Drug Systemic Exposure
Coadministered Drug | Dosing of Coadministered Drug* | Dosing of Metformin* | Geometric Mean Ratio (ratio with/without metformin) No effect=1.0
 |  |  |  | AUC† | Cmax
Glyburide | 5 mg | 850 mg | glyburide | 0.78‡ | 0.63‡
Furosemide | 40 mg | 850 mg | furosemide | 0.87‡ | 0.69‡
Nifedipine | 10 mg | 850 mg | nifedipine | 1.10§ | 1.08
Propranolol | 40 mg | 850 mg | propranolol | 1.01§ | 1.02
Ibuprofen | 400 mg | 850 mg | ibuprofen | 0.97¶ | 1.01¶
Cimetidine | 400 mg | 850 mg | cimetidine | 0.95§ | 1.01
*All metformin and coadministered drugs were given as single doses
†AUC=AUC(INF) unless otherwise noted
‡Ratio of arithmetic means, p-value of difference <0.05
§AUC(0-24 hours) reported
¶Ratio of arithmetic means

13 NONCLINICAL TOXICOLOGY

13.1 Carcinogenesis, Mutagenesis, Impairment of Fertility

JENTADUETO

No carcinogenicity, mutagenicity, or impairment of fertility studies have been conducted with the combination of linagliptin and metformin HCl.

Linagliptin

Linagliptin did not increase the incidence of tumors in male and female rats in a 2-year study at doses of 6, 18, and 60 mg/kg. The highest dose of 60 mg/kg is approximately 418 times the clinical dose of 5 mg/day based on AUC exposure. Linagliptin did not increase the incidence of tumors in mice in a 2-year study at doses up to 80 mg/kg (males) and 25 mg/kg (females), or approximately 35 and 270 times the clinical dose based on AUC exposure. Higher doses of linagliptin in female mice (80 mg/kg) increased the incidence of lymphoma at approximately 215 times the clinical dose based on AUC exposure.

Linagliptin was not mutagenic or clastogenic with or without metabolic activation in the Ames bacterial mutagenicity assay, a chromosomal aberration test in human lymphocytes, and an in vivo micronucleus assay.

In fertility studies in rats, linagliptin had no adverse effects on early embryonic development, mating, fertility, or bearing live young up to the highest dose of 240 mg/kg (approximately 943 times the clinical dose based on AUC exposure).

Metformin HCl

Long-term carcinogenicity studies have been performed in rats (dosing duration of 104 weeks) and mice (dosing duration of 91 weeks) at doses up to and including 900 mg/kg/day and 1,500 mg/kg/day, respectively. These doses are both approximately 4 times the maximum recommended human daily dose of 2,000 mg/kg/day based on body surface area comparisons. No evidence of carcinogenicity with metformin was found in either male or female mice. Similarly, there was no tumorigenic potential observed with metformin in male rats. There was, however, an increased incidence of benign stromal uterine polyps in female rats treated with 900 mg/kg/day.

There was no evidence of a mutagenic potential of metformin in the following in vitro tests: Ames test (Salmonella typhimurium), gene mutation test (mouse lymphoma cells), or chromosomal aberrations test (human lymphocytes). Results in the in vivo mouse micronucleus test were also negative.

Fertility of male or female rats was unaffected by metformin when administered at doses as high as 600 mg/kg/day, which is approximately 2 times the MRHD based on body surface area comparisons.

14 CLINICAL STUDIES

14.1 Glycemic Control Trials in Adults with Type 2 Diabetes Mellitus

Initial Combination Therapy with Linagliptin and Metformin

A total of 791 patients with type 2 diabetes mellitus and inadequate glycemic control on diet and exercise participated in the 24-week, randomized, double-blind, portion of this placebo-controlled factorial trial designed to assess the efficacy of linagliptin as initial therapy with metformin. Patients on an antihyperglycemic agent (52%) underwent a drug washout period of 4 weeks' duration. After the washout period and after completing a 2-week single-blind placebo run-in period, patients with inadequate glycemic control (A1C ≥7.0% to ≤10.5%) were randomized. Patients with inadequate glycemic control (A1C ≥7.5% to <11.0%) not on antihyperglycemic agents at trial entry (48%) immediately entered the 2-week single-blind placebo run-in period and then were randomized. Randomization was stratified by baseline A1C (<8.5% vs ≥8.5%) and use of a prior oral antidiabetic drug (none vs monotherapy). Patients were randomized in a 1:2:2:2:2:2 ratio to either placebo or one of 5 active-treatment arms. Approximately equal numbers of patients were randomized to receive initial therapy with 5 mg of linagliptin once daily, 500 mg or 1,000 mg of metformin twice daily, or 2.5 mg of linagliptin twice daily in combination with 500 mg or 1,000 mg of metformin twice daily. Patients who failed to meet specific glycemic goals during the trial were treated with sulfonylurea, thiazolidinedione, or insulin rescue therapy.

Initial therapy with the combination of linagliptin and metformin provided significant improvements in A1C, and fasting plasma glucose (FPG) compared to placebo, to metformin alone, and to linagliptin alone (Table 7, Figure 1). The adjusted mean treatment difference in A1C from baseline to week 24 (LOCF) was -0.5% (95% CI -0.7, -0.3; p<0.0001) for linagliptin 2.5 mg/metformin 1,000 mg twice daily compared to metformin 1,000 mg twice daily; -1.1% (95% CI -1.4, -0.9; p<0.0001) for linagliptin 2.5 mg/metformin 1,000 mg twice daily compared to linagliptin 5 mg once daily; -0.6% (95% CI -0.8, -0.4; p<0.0001) for linagliptin 2.5 mg/metformin 500 mg twice daily compared to metformin 500 mg twice daily; and -0.8% (95% CI -1.0, -0.6; p<0.0001) for linagliptin 2.5 mg/metformin 500 mg twice daily compared to linagliptin 5 mg once daily.

Lipid effects were generally neutral. No meaningful change in body weight was noted in any of the 6 treatment groups.

Table 7 Glycemic Parameters at Final Visit (24-Week Trial) for Linagliptin and Metformin, Alone and in Combination in Randomized Patients with Type 2 Diabetes Mellitus Inadequately Controlled on Diet and Exercise**
 | Placebo | Linagliptin 5 mg Once Daily* | Metformin 500 mg Twice Daily | Linagliptin 2.5 mg Twice Daily* + Metformin 500 mg Twice Daily | Metformin 1,000 mg Twice Daily | Linagliptin 2.5 mg Twice Daily* + Metformin 1,000 mg Twice Daily
A1C (%)
Number of patients | n=65 | n=135 | n=141 | n=137 | n=138 | n=140
Baseline (mean) | 8.7 | 8.7 | 8.7 | 8.7 | 8.5 | 8.7
Change from baseline (adjusted mean****) | 0.1 | -0.5 | -0.6 | -1.2 | -1.1 | -1.6
Difference from placebo (adjusted mean) (95% CI) | -- | -0.6 (-0.9, -0.3) | -0.8 (-1.0, -0.5) | -1.3 (-1.6, -1.1) | -1.2 (-1.5, -0.9) | -1.7 (-2.0, -1.4)
Patients [n (%)] achieving A1C <7%*** | 7 (10.8) | 14 (10.4) | 26 (18.6) | 41 (30.1) | 42 (30.7) | 74 (53.6)
Patients (%) receiving rescue medication | 29.2 | 11.1 | 13.5 | 7.3 | 8.0 | 4.3
FPG (mg/dL)
Number of patients | n=61 | n=134 | n=136 | n=135 | n=132 | n=136
Baseline (mean) | 203 | 195 | 191 | 199 | 191 | 196
Change from baseline (adjusted mean****) | 10 | -9 | -16 | -33 | -32 | -49
Difference from placebo (adjusted mean) (95% CI) | -- | -19 (-31, -6) | -26 (-38, -14) | -43 (-56, -31) | -42 (-55, -30) | -60 (-72, -47)
*Total daily dosage of linagliptin is equal to 5 mg
**Full analysis population using last observation on trial
***Metformin 500 mg twice daily, n=140; Linagliptin 2.5 mg twice daily + Metformin 500 mg twice daily, n=136; Metformin 1,000 mg twice daily, n=137; Linagliptin 2.5 mg twice daily + Metformin 1,000 mg twice daily, n=138
****HbA1c: ANCOVA model included treatment and number of prior OADs as class-effects, as well as baseline HbA1c as continuous covariates. FPG: ANCOVA model included treatment and number of prior OADs as class-effects, as well as baseline HbA1c and baseline FPG as continuous covariates.

Figure 1 Adjusted Mean Change from Baseline for A1C (%) over 24 Weeks with Linagliptin and Metformin, Alone and in Combination in Patients with Type 2 Diabetes Mellitus Inadequately Controlled with Diet and Exercise - FAS completers

Initial Combination Therapy with Linagliptin and Metformin vs Linagliptin in Treatment-Naïve Patients

A total of 316 patients with type 2 diabetes mellitus diagnosed within the previous 12 months and treatment-naïve (no antidiabetic therapy for 12 weeks prior to randomization) and inadequate glycemic control (A1C ≥8.5% to ≤12.0%) participated in a 24-week, randomized, double-blind, trial designed to assess the efficacy of linagliptin in combination with metformin vs linagliptin. Patients were randomized (1:1), after a 2-week run-in period, to either linagliptin 5 mg plus metformin (1,500 to 2,000 mg per day, n=159) or linagliptin 5 mg plus placebo, (n=157) administered once daily. Patients in the linagliptin and metformin treatment group were up-titrated to a maximum tolerated dosage of metformin (1,000 to 2,000 mg per day) over a three-week period.

Initial therapy with the combination of linagliptin and metformin provided statistically significant improvements in A1C compared to linagliptin (Table 8). The mean difference between groups in A1C change from baseline was -0.8% with 2-sided 95% confidence interval (-1.23%, -0.45%).

Table 8 Glycemic Parameters at 24 Weeks in Trial Comparing Linagliptin in Combination with Metformin to Linagliptin in Treatment-Naïve Patients*
 | Linagliptin 5 mg + Metformin | Linagliptin 5 mg + Placebo
A1C (%)*
Number of patients | n=153 | n=150
Baseline (mean) | 9.8 | 9.9
Change from baseline (adjusted mean) | -2.9 | -2
Difference from linagliptin (adjusted mean**) (95% CI) | -0.84† (-1.23, -0.45) | --
Patients [n (%)] achieving A1C <7%* | 82 (53.6) | 45 (30)
FPG (mg/dL)*
Number of patients | n=153 | n=150
Baseline (mean) | 196 | 198
Change from baseline (adjusted mean) | -54 | -35
Difference from linagliptin (adjusted mean**) (95% CI) | -18†† (-31, -5.5) | --
†p<0.0001 compared to linagliptin, ††p=0.0054 compared to linagliptin
*Full analysis set population
**A1C: MMRM model included treatment, continuous baseline A1C, baseline A1C by visit interaction, visit by treatment interaction, baseline renal impairment by treatment interaction and baseline renal impairment by treatment by visit interaction. FPG: MMRM model included treatment, continuous baseline A1C, continuous baseline FPG, baseline FPG by visit interaction, visit by treatment interaction, baseline renal impairment by treatment interaction and baseline renal impairment by treatment by visit interaction.

The adjusted mean changes for A1C (%) from baseline over time for linagliptin and metformin as compared to linagliptin alone were maintained throughout the 24-week treatment period. Using the completers analysis the respective adjusted means for A1C (%) changes from baseline for linagliptin and metformin as compared to linagliptin alone were -1.9 and -1.3 at week 6, -2.6 and -1.8 at week 12, -2.7 and -1.9 at week 18, and -2.7 and -1.9 at week 24.

Changes in body weight from baseline were not clinically significant in either treatment group.

Add-On Combination Therapy with Metformin

A total of 701 patients with type 2 diabetes mellitus participated in a 24-week, randomized, double-blind, placebo-controlled trial designed to assess the efficacy of linagliptin in combination with metformin. Patients already on metformin (n=491) at a dosage of at least 1,500 mg per day were randomized after completing a 2-week, open-label, placebo run-in period. Patients on metformin and another antihyperglycemic agent (n=207) were randomized after a run-in period of approximately 6 weeks on metformin (at a dosage of at least 1,500 mg per day) in monotherapy. Patients were randomized to the addition of either linagliptin 5 mg or placebo, administered once daily. Patients who failed to meet specific glycemic goals during the studies were treated with glimepiride rescue.

In combination with metformin, linagliptin provided statistically significant improvements in A1C, FPG, and 2-hour PPG compared with placebo (Table 9). Rescue glycemic therapy was used in 7.8% of patients treated with linagliptin 5 mg and in 18.9% of patients treated with placebo. A similar decrease in body weight was observed for both treatment groups.

Table 9 Glycemic Parameters in Placebo-Controlled Trial for Linagliptin in Combination with Metformin*
 | Linagliptin 5 mg + Metformin | Placebo + Metformin
A1C (%)
Number of patients | n=513 | n=175
Baseline (mean) | 8.1 | 8.0
Change from baseline (adjusted mean***) | -0.5 | 0.15
Difference from placebo + metformin (adjusted mean) (95% CI) | -0.6 (-0.8, -0.5) | --
Patients [n (%)] achieving A1C <7%** | 127 (26.2) | 15 (9.2)
FPG (mg/dL)
Number of patients | n=495 | n=159
Baseline (mean) | 169 | 164
Change from baseline (adjusted mean***) | -11 | 11
Difference from placebo + metformin (adjusted mean) (95% CI) | -21 (-27, -15) | --
2-hour PPG (mg/dL)
Number of patients | n=78 | n=21
Baseline (mean) | 270 | 274
Change from baseline (adjusted mean***) | -49 | 18
Difference from placebo + metformin (adjusted mean) (95% CI) | -67 (-95, -40) | --
* Full analysis population using last observation on trial
**Linagliptin 5 mg + Metformin, n=485; Placebo + Metformin, n=163
***HbA1c: ANCOVA model included treatment and number of prior oral OADs as class-effects, as well as baseline HbA1c as continuous covariates. FPG: ANCOVA model included treatment and number of prior OADs as class-effects, as well as baseline HbA1c and baseline FPG as continuous covariates. PPG: ANCOVA model included treatment and number of prior OADs as class-effects, as well as baseline HbA1c and baseline postprandial glucose after two hours as covariate.

Active-Controlled Trial vs Glimepiride in Combination with Metformin

The efficacy of linagliptin was evaluated in a 104-week, double-blind, glimepiride-controlled non-inferiority trial in type 2 diabetic patients with insufficient glycemic control despite metformin therapy. Patients being treated with metformin only entered a run-in period of 2 weeks' duration, whereas patients pretreated with metformin and one additional antihyperglycemic agent entered a run-in treatment period of 6 weeks' duration with metformin monotherapy (dosage of ≥1,500 mg per day) and washout of the other agent. After an additional 2-week placebo run-in period, those with inadequate glycemic control (A1C 6.5% to 10%) were randomized 1:1 to the addition of linagliptin 5 mg once daily or glimepiride. Randomization was stratified by baseline HbA1c (<8.5% vs ≥8.5%), and the previous use of antidiabetic drugs (metformin alone vs metformin plus one other OAD). Patients receiving glimepiride were given an initial dosage of 1 mg/day and then electively titrated over the next 12 weeks to a maximum dosage of 4 mg/day as needed to optimize glycemic control. Thereafter, the glimepiride dosage was to be kept constant, except for down-titration to prevent hypoglycemia.

After 52 weeks and 104 weeks, linagliptin and glimepiride both had reductions from baseline in A1C (52 weeks: -0.4% for linagliptin, -0.6% for glimepiride; 104 weeks: -0.2% for linagliptin, -0.4% for glimepiride) from a baseline mean of 7.7% (Table 10). The mean difference between groups in A1C change from baseline was 0.2% with 2-sided 97.5% confidence interval (0.1%, 0.3%) for the intent-to-treat population using last observation carried forward. These results were consistent with the completers analysis.

Table 10 Glycemic Parameters at 52 and 104 Weeks in Trial Comparing Linagliptin to Glimepiride as Add-On Therapy in Patients Inadequately Controlled on Metformin**
 | Week 52 |  | Week 104
 | Linagliptin 5 mg + Metformin | Glimepiride + Metformin (mean glimepiride dosage 3 mg) | Linagliptin 5 mg + Metformin | Glimepiride + Metformin (mean glimepiride dosage 3 mg)
A1C (%)
Number of patients | n=764 | n=755 | n=764 | n=755
Baseline (mean) | 7.7 | 7.7 | 7.7 | 7.7
Change from baseline (adjusted mean***) | -0.4 | -0.6 | -0.2 | -0.4
Difference from glimepiride (adjusted mean) (97.5% CI) | 0.2 (0.1, 0.3) | -- | 0.2 (0.1, 0.3) | --
FPG (mg/dL)
Number of patients | n=733 | n=725 | n=733 | n=725
Baseline (mean) | 164 | 166 | 164 | 166
Change from baseline (adjusted mean***) | -8* | -15 | -2† | -9
*p<0.0001 vs glimepiride; †p=0.0012 vs glimepiride
**Full analysis population using last observation on trial
***HbA1c: ANCOVA model included treatment and number of prior OADs as class-effects, as well as baseline HbA1c as continuous covariates. FPG: ANCOVA model included treatment and number of prior OADs as class-effects, as well as baseline HbA1c and baseline FPG as continuous covariates.

Patients treated with linagliptin had a mean baseline body weight of 86 kg and were observed to have an adjusted mean decrease in body weight of 1.1 kg at 52 weeks and 1.4 kg at 104 weeks. Patients on glimepiride had a mean baseline body weight of 87 kg and were observed to have an adjusted mean increase from baseline in body weight of 1.4 kg at 52 weeks and 1.3 kg at 104 weeks (treatment difference p<0.0001 for both timepoints).

Add-On Combination Therapy with Metformin and a Sulfonylurea

A total of 1,058 patients with type 2 diabetes mellitus participated in a 24-week, randomized, double-blind, placebo-controlled trial designed to assess the efficacy of linagliptin in combination with a sulfonylurea and metformin. The most common sulfonylureas used by patients in the trial were glimepiride (31%), glibenclamide (26%), and gliclazide (26% [not available in the United States]). Patients on a sulfonylurea and metformin were randomized to receive linagliptin 5 mg or placebo, each administered once daily. Patients who failed to meet specific glycemic goals during the trial were treated with pioglitazone rescue. Glycemic end points measured included A1C and FPG.

In combination with a sulfonylurea and metformin, linagliptin provided statistically significant improvements in A1C and FPG compared with placebo (Table 11). In the entire trial population (patients on linagliptin in combination with a sulfonylurea and metformin), a mean reduction from baseline relative to placebo in A1C of -0.6% and in FPG of -13 mg/dL was seen. Rescue therapy was used in 5.4% of patients treated with linagliptin 5 mg and in 13% of patients treated with placebo. Change from baseline in body weight did not differ significantly between the groups.

Table 11 Glycemic Parameters at Final Visit (24-Week Trial) for Linagliptin in Combination with Metformin and Sulfonylurea*
 | Linagliptin 5 mg + Metformin + SU | Placebo + Metformin + SU
A1C (%)
Number of patients | n=778 | n=262
Baseline (mean) | 8.2 | 8.1
Change from baseline (adjusted mean***) | -0.7 | -0.1
Difference from placebo (adjusted mean) (95% CI) | -0.6 (-0.7, -0.5) | --
Patients [n (%)] achieving A1C <7%** | 217 (29.2) | 20 (8.1)
FPG (mg/dL)
Number of patients | n=739 | n=248
Baseline (mean) | 159 | 163
Change from baseline (adjusted mean***) | -5 | 8
Difference from placebo (adjusted mean) (95% CI) | -13 (-18, -7) | --
SU=sulfonylurea
*Full analysis population using last observation on trial
**Linagliptin 5 mg + Metformin + SU, n=742; Placebo + Metformin + SU, n=247
***HbA1c: ANCOVA model included treatment as class-effects and baseline HbA1c as continuous covariates. FPG: ANCOVA model included treatment as class-effects, as well as baseline HbA1c and baseline FPG as continuous covariates.

14.2 Linagliptin Cardiovascular Safety Trials in Patients with Type 2 Diabetes Mellitus

CARMELINA

The cardiovascular risk of linagliptin was evaluated in CARMELINA, a multi-national, multi-center, placebo-controlled, double-blind, parallel group trial comparing linagliptin (N=3,494) to placebo (N=3,485) in adult patients with type 2 diabetes mellitus and a history of established macrovascular and/or renal disease. The trial compared the risk of major adverse cardiovascular events (MACE) between linagliptin and placebo when these were added to standard of care treatments for diabetes mellitus and other cardiovascular risk factors. The trial was event driven, the median duration of follow-up was 2.2 years and vital status was obtained for 99.7% of patients.

Patients were eligible to enter the trial if they were adults with type 2 diabetes mellitus, with HbA1c of 6.5% to 10%, and had either albuminuria and previous macrovascular disease (39% of enrolled population), or evidence of impaired renal function by eGFR and Urinary Albumin Creatinine Ratio (UACR) criteria (42% of enrolled population), or both (18% of enrolled population).

At baseline the mean age was 66 years and the population was 63% male, 80% White, 9% Asian, 6% Black or African American and 36% were of Hispanic or Latino ethnicity. Mean HbA1c was 8.0% and mean duration of type 2 diabetes mellitus was 15 years. The trial population included 17% patients ≥75 years of age and 62% patients with renal impairment defined as eGFR <60 mL/min/1.73 m^2. The mean eGFR was 55 mL/min/1.73 m^2 and 27% of patients had mild renal impairment (eGFR 60 to 90 mL/min/1.73 m^2), 47% of patients had moderate renal impairment (eGFR 30 to <60 mL/min/1.73 m^2) and 15% of patients had severe renal impairment (eGFR <30 mL/min/1.73 m^2). Patients were taking at least one antidiabetic drug (97%), and the most common were insulin and analogues (57%), metformin (54%) and sulfonylurea (32%). Patients were also taking antihypertensives (96%), lipid lowering drugs (76%) with 72% on statin, and aspirin (62%).

The primary endpoint, MACE, was the time to first occurrence of one of three composite outcomes which included cardiovascular death, non-fatal myocardial infarction or non-fatal stroke. The trial was designed as a non-inferiority trial with a pre-specified risk margin of 1.3 for the hazard ratio of MACE.

The results of CARMELINA, including the contribution of each component to the primary composite endpoint, are shown in Table 12. The estimated hazard ratio for MACE associated with linagliptin relative to placebo was 1.02 with a 95% confidence interval of (0.89, 1.17). The upper bound of this confidence interval, 1.17, excluded the risk margin of 1.3. The Kaplan-Meier curve depicting time to first occurrence of MACE is shown in Figure 2.

Table 12 Major Adverse Cardiovascular Events (MACE) by Treatment Group in the CARMELINA Trial
 | Linagliptin 5 mg n = 3,494 |  | Placebo n = 3,485 |  | Hazard Ratio
 | Number of Subjects (%) | Incidence Rate per 1,000 PY* | Number of Subjects (%) | Incidence Rate per 1,000 PY* | (95% CI)
Composite of first event of CV death, non-fatal myocardial infarction (MI), or non-fatal stroke (MACE) | 434 (12.4) | 57.7 | 420 (12.1) | 56.3 | 1.02 (0.89, 1.17)
CV death** | 255 (7.3) | 32.6 | 264 (7.6) | 34.0 | 0.96 (0.81, 1.14)
Non-fatal MI** | 156 (4.5) | 20.6 | 135 (3.9) | 18.0 | 1.15 (0.91, 1.45)
Non-fatal stroke** | 65 (1.9) | 8.5 | 73 (2.1) | 9.6 | 0.88 (0.63, 1.23)
*PY=patient years
**A patient may have experienced more than one component; therefore, the sum of the components is larger than the number of patients who experienced the composite outcome.

Figure 2 Kaplan-Meier: Time to First Occurrence of MACE in the CARMELINA Trial

CAROLINA

The cardiovascular risk of linagliptin was evaluated in CAROLINA, a multi-center, multi-national, randomized, double-blind, parallel group trial comparing linagliptin (N=3,023) to glimepiride (N=3,010) in adult patients with type 2 diabetes mellitus and a history of established cardiovascular disease and/or multiple cardiovascular risk factors. The trial compared the risk of major adverse cardiovascular events (MACE) between linagliptin and glimepiride when these were added to standard of care treatments for diabetes mellitus and other cardiovascular risk factors. The trial was event driven, the median duration of follow-up was 6.23 years and vital status was obtained for 99.3% of patients.

Patients were eligible to enter the trial if they were adults with type 2 diabetes mellitus with insufficient glycemic control (defined as HbA1c of 6.5% to 8.5% or 6.5% to 7.5% depending on whether treatment-naïve, on monotherapy or on combination therapy), and were defined to be at high cardiovascular risk with previous vascular disease, evidence of vascular related end-organ damage, age ≥70 years, and/or two cardiovascular risk factors (duration of diabetes mellitus >10 years, systolic blood pressure >140 mmHg, current smoker, LDL cholesterol ≥135 mg/dL).

At baseline, the mean age was 64 years and the population was 60% male, 73% White, 18% Asian, 5% Black or African American, and 17% were of Hispanic or Latino ethnicity. The mean HbA1c was 7.15% and mean duration of type 2 diabetes mellitus was 7.6 years. The trial population included 34% patients ≥70 years of age and 19% patients with renal impairment defined as eGFR <60 mL/min/1.73 m^2. The mean eGFR was 77 mL/min/1.73 m^2. Patients were taking at least one antidiabetic drug (91%) and the most common were metformin (83%) and sulfonylurea (28%). Patients were also taking antihypertensives (89%), lipid lowering drugs (70%) with 65% on statin, and aspirin (47%).

The primary endpoint, MACE, was the time to first occurrence of one of three composite outcomes which included cardiovascular death, non-fatal myocardial infarction or non-fatal stroke. The trial was designed as a non-inferiority trial with a pre-specified risk margin of 1.3 for the upper bound of the 95% CI for the hazard ratio of MACE.

The results of CAROLINA, including the contribution of each component to the primary composite endpoint, are shown in Table 13. The Kaplan-Meier curve depicting time to first occurrence of MACE is shown in Figure 3.

Table 13 Major Adverse Cardiovascular Events (MACE) by Treatment Group in the CAROLINA Trial
 | Linagliptin 5 mg n=3,023 |  | Glimepiride (1 mg to 4 mg) n=3,010 |  | Hazard Ratio
 | Number of Subjects (%) | Incidence Rate per 1,000 PY* | Number of Subjects (%) | Incidence Rate per 1,000 PY* | (95% CI)
Composite of first event of CV death, non-fatal myocardial infarction (MI), or non-fatal stroke (MACE) | 356 (11.8) | 20.7 | 362 (12.0) | 21.2 | 0.98 (0.84, 1.14)
CV death** | 169 (5.6) | 9.2 | 168 (5.6) | 9.2 | 1.00 (0.81, 1.24)
Non-fatal MI** | 145 (4.8) | 8.3 | 142 (4.7) | 8.2 | 1.01 (0.80, 1.28)
Non-fatal stroke** | 91 (3.0) | 5.2 | 104 (3.5) | 6.0 | 0.87 (0.66, 1.15)
*PY=patient years
**A patient may have experienced more than one component; therefore, the sum of the components is larger than the number of patients who experienced the composite outcome

Figure 3 Time to First Occurrence of 3P-MACE in CAROLINA

16 HOW SUPPLIED/STORAGE AND HANDLING

JENTADUETO (linagliptin and metformin HCl) tablets 2.5 mg/500 mg are light yellow, oval, biconvex tablets debossed with "D2/500" on one side and the Boehringer Ingelheim symbol on the other side, and are supplied as follows:
Bottles of 60 (NDC 0597-0146-60)
Bottles of 180 (NDC 0597-0146-18)

JENTADUETO (linagliptin and metformin HCl) tablets 2.5 mg/850 mg are light orange, oval, biconvex tablets debossed with "D2/850" on one side and the Boehringer Ingelheim symbol on the other side, and are supplied as follows:
Bottles of 60 (NDC 0597-0147-60)
Bottles of 180 (NDC 0597-0147-18)

JENTADUETO (linagliptin and metformin HCl) tablets 2.5 mg/1,000 mg are light pink, oval, biconvex tablets debossed with "D2/1000" on one side and the Boehringer Ingelheim symbol on the other side, and are supplied as follows:
Bottles of 60 (NDC 0597-0148-60)
Bottles of 180 (NDC 0597-0148-18)

Storage

Store at 20°C to 25°C (68°F to 77°F); excursions permitted to 15°C to 30°C (59°F to 86°F) [see USP Controlled Room Temperature]. Protect from exposure to high humidity.

17 PATIENT COUNSELING INFORMATION

Advise the patient to read the FDA-approved patient labeling (Medication Guide)

Lactic Acidosis

Inform patients of the risks of lactic acidosis due to metformin, its symptoms, and conditions that predispose to its development. Advise patients to discontinue JENTADUETO immediately and to notify their healthcare provider promptly if unexplained hyperventilation, malaise, myalgia, unusual somnolence, or other nonspecific symptoms occur. Counsel patients against excessive alcohol intake and inform patients about importance of regular testing of renal function while receiving JENTADUETO. Instruct patients to inform their healthcare provider that they are taking JENTADUETO prior to any surgical or radiological procedure, as temporary discontinuation may be required until renal function has been confirmed to be normal [see Warnings and Precautions (5.1)].

Pancreatitis

Inform patients that acute pancreatitis has been reported during use of linagliptin. Inform patients that persistent severe abdominal pain, sometimes radiating to the back, which may or may not be accompanied by vomiting, is the hallmark symptom of acute pancreatitis. Instruct patients to discontinue JENTADUETO promptly and contact their healthcare provider if persistent severe abdominal pain occurs [see Warnings and Precautions (5.2)].

Hypoglycemia with Concomitant Use with Insulin and Insulin Secretagogues

Inform patients that the risk of hypoglycemia is increased when JENTADUETO is used in combination with an insulin secretagogue (e.g., sulfonylurea) or insulin [see Warnings and Precautions (5.3)].

Hypersensitivity Reactions

Inform patients that serious allergic reactions, such as anaphylaxis, angioedema, and exfoliative skin conditions, have been reported during postmarketing use of linagliptin (one of the components of JENTADUETO). If symptoms of allergic reactions (such as rash, skin flaking or peeling, urticaria, swelling of the skin, or swelling of the face, lips, tongue, and throat that may cause difficulty in breathing or swallowing) occur, patients must stop taking JENTADUETO and seek medical advice promptly [see Warnings and Precautions (5.4)].

Vitamin B12 Deficiency

Inform patients about the importance of regular hematological parameters while receiving JENTADUETO [see Warnings and Precautions (5.5)].

Severe and Disabling Arthralgia

Inform patients that severe and disabling joint pain may occur with this class of drugs. The time to onset of symptoms can range from one day to years. Instruct patients to seek medical advice if severe joint pain occurs [see Warnings and Precautions (5.6)].

Bullous Pemphigoid

Inform patients that bullous pemphigoid has been reported during use of linagliptin. Instruct patients to seek medical advice if blisters or erosions occur [see Warnings and Precautions (5.7)].

Heart Failure

Inform patients of the signs and symptoms of heart failure. Before initiating JENTADUETO, patients should be asked about a history of heart failure or other risk factors for heart failure including moderate to severe renal impairment. Instruct patients to contact their healthcare provider as soon as possible if they experience symptoms of heart failure, including increasing shortness of breath, rapid increase in weight or swelling of the feet [see Warnings and Precautions (5.8)].

Patients of Reproductive Potential

Inform patients that treatment with metformin may result in ovulation in some premenopausal anovulatory patients, which may lead to unintended pregnancy [see Use in Specific Populations (8.3)].

Missed Dose

Instruct patients to take JENTADUETO only as prescribed. If a dose is missed, it should be taken as soon as the patient remembers. Advise patients not to double their next dose.

Distributed by:
Boehringer Ingelheim Pharmaceuticals, Inc.
Ridgefield, CT 06877 USA

Licensed from:
Boehringer Ingelheim International GmbH, Ingelheim, Germany

JENTADUETO is a registered trademark of and used under license from Boehringer Ingelheim International GmbH.

Boehringer Ingelheim Pharmaceuticals, Inc. either owns or uses the Tradjenta®, CARMELINA®, and CAROLINA® trademarks under license.

The other brands listed are trademarks of their respective owners and are not trademarks of Boehringer Ingelheim Pharmaceuticals, Inc.

Copyright © 2023 Boehringer Ingelheim International GmbH
ALL RIGHTS RESERVED

COL9414DF212023
SPL9435E

MEDICATION GUIDE
JENTADUETO® (JEN ta doo e toe)
(linagliptin and metformin hydrochloride tablets)
for oral use

What is the most important information I should know about JENTADUETO?

JENTADUETO can cause serious side effects, including:

1. Lactic acidosis. Metformin hydrochloride (HCl), one of the medicines in JENTADUETO, can cause a rare but serious condition called lactic acidosis (a build-up of lactic acid in the blood) that can cause death. Lactic acidosis is a medical emergency and must be treated in a hospital.
  Stop taking JENTADUETO and call your healthcare provider right away or go to the nearest hospital emergency room if you get any of the following symptoms of lactic acidosis:

- feel very weak and tired
- have unusual (not normal) muscle pain
- have trouble breathing
- have unexplained stomach or intestinal problems with nausea and vomiting, or diarrhea

- have unusual sleepiness or sleep longer than usual
- feel cold, especially in your arms and legs
- feel dizzy or lightheaded
- have a slow or irregular heartbeat

You have a higher chance of getting lactic acidosis with JENTADUETO if you:

- have severe kidney problems.
- have liver problems.
- drink a lot of alcohol (very often or short-term "binge" drinking).
- get dehydrated (lose a large amount of body fluids). This can happen if you are sick with a fever, vomiting, or diarrhea. Dehydration can also happen when you sweat a lot with activity or exercise and do not drink enough fluids.
- have certain x-ray tests with injectable dyes or contrast agents.
- have surgery or other procedures for which you need to restrict the amount of food and liquid you eat and drink.
- have congestive heart failure.
- have a heart attack, severe infection, or stroke.
- are 65 years of age or older.

Tell your healthcare provider if you have any of the problems in the list above. Tell your healthcare provider that you are taking JENTADUETO before you have surgery or x-ray tests. Your healthcare provider may decide to stop your JENTADUETO for a while if you have surgery or certain x-ray tests. JENTADUETO can have other serious side effects. See "What are the possible side effects of JENTADUETO?"

2. Inflammation of the pancreas (pancreatitis) which may be severe and lead to death. Certain medical problems make you more likely to get pancreatitis.

Before you start taking JENTADUETO, tell your healthcare provider if you have ever had:

- inflammation of your pancreas (pancreatitis)
- a history of alcoholism

- stones in your gallbladder (gallstones)
- high blood triglyceride levels

Stop taking JENTADUETO and call your healthcare provider right away if you have pain in your stomach area (abdomen) that is severe and will not go away. The pain may be felt going from your abdomen to your back. The pain may happen with or without vomiting. These may be symptoms of pancreatitis.

What is JENTADUETO?

- JENTADUETO is a prescription medicine that contains 2 diabetes medicines, linagliptin (TRADJENTA) and metformin HCl. JENTADUETO can be used along with diet and exercise to lower blood sugar in adults with type 2 diabetes mellitus.
- JENTADUETO is not for people with type 1 diabetes mellitus.
- If you have had pancreatitis in the past, it is not known if you have a higher chance of getting pancreatitis while you take JENTADUETO.
- It is not known if JENTADUETO is safe and effective in children.

Who should not take JENTADUETO?

Do not take JENTADUETO if you:

- have severe kidney problems.
- have a condition called metabolic acidosis or diabetic ketoacidosis (increased ketones in the blood or urine).
- are allergic to linagliptin (TRADJENTA), metformin, or any of the ingredients in JENTADUETO. See the end of this Medication Guide for a complete list of ingredients in JENTADUETO.
  Symptoms of a serious allergic reaction to JENTADUETO may include:
  - skin rash, itching, flaking or peeling
  - raised red patches on your skin (hives)
  - swelling of your face, lips, tongue and throat that may cause difficulty in breathing or swallowing
  - difficulty with swallowing or breathing
  If you have any of these symptoms, stop taking JENTADUETO and call your healthcare provider right away or go to the nearest hospital emergency room.

What should I tell my healthcare provider before taking JENTADUETO?

Before taking JENTADUETO, tell your healthcare provider about all of your medical conditions, including if you:

- have or have had inflammation of your pancreas (pancreatitis).
- have kidney problems.
- have liver problems.
- have heart problems, including congestive heart failure.
- are 65 years of age or older.
- drink alcohol very often, or drink a lot of alcohol in short term ("binge" drinking).
- are going to get an injection of dye or contrast agents for an x-ray procedure. JENTADUETO may need to be stopped for a short time. Talk to your healthcare provider about when you should stop JENTADUETO and when you should start JENTADUETO again. See "What is the most important information I should know about JENTADUETO?"
- have type 1 diabetes mellitus. JENTADUETO should not be used to treat people with type 1 diabetes mellitus.
- have low levels of vitamin B12 in your blood.
- are pregnant or plan to become pregnant. It is not known if JENTADUETO will harm your unborn baby. If you are pregnant, talk with your healthcare provider about the best way to control your blood sugar while you are pregnant.
- are breastfeeding or plan to breastfeed. JENTADUETO may pass into your breast milk and may harm your baby. Talk with your healthcare provider about the best way to feed your baby if you take JENTADUETO.
- are a person who has not gone through menopause (premenopausal) who does not have periods regularly or at all. JENTADUETO can cause the release of an egg from an ovary in a person (ovulation). This can increase your chance of getting pregnant. Tell your healthcare provider right away if you become pregnant while taking JENTADUETO.

Tell your healthcare provider about all the medicines you take, including prescription and over-the-counter medicines, vitamins, and herbal supplements.

JENTADUETO may affect the way other medicines work, and other medicines may affect how JENTADUETO works.

Know the medicines you take. Keep a list of them to show your healthcare provider and pharmacist when you get a new medicine.

How should I take JENTADUETO?

- Take JENTADUETO exactly as your healthcare provider tells you to take it.
- Take JENTADUETO 2 times each day with meals. Taking JENTADUETO with meals may lower your chance of having an upset stomach.
- If you miss a dose, take it with food as soon as you remember. If you do not remember until it is time for your next dose, skip the missed dose and go back to your regular schedule. Do not take 2 doses of JENTADUETO at the same time.
- If you take too much JENTADUETO, call your healthcare provider or local poison control center or go to the nearest hospital emergency room right away.
- Your healthcare provider may tell you to take JENTADUETO along with other diabetes medicines. Low blood sugar can happen more often when JENTADUETO is taken with certain other diabetes medicines. See "What are the possible side effects of JENTADUETO?"
- Your healthcare provider will do blood tests to check how well your kidneys are working before and during your treatment with JENTADUETO.

What should I avoid while taking JENTADUETO?
Avoid drinking alcohol very often or drinking a lot of alcohol in a short period of time ("binge" drinking). It can increase your chances of getting serious side effects.

What are the possible side effects of JENTADUETO?

JENTADUETO may cause serious side effects, including:

- See "What is the most important information I should know about JENTADUETO?"
- Low blood sugar (hypoglycemia). If you take JENTADUETO with another medicine that can cause low blood sugar, such as a sulfonylurea or insulin, your risk of getting low blood sugar is higher. The dose of your sulfonylurea medicine or insulin may need to be lowered while you take JENTADUETO. Signs and symptoms of low blood sugar may include:

- headache
- fast heartbeat

- irritability
- dizziness

- drowsiness
- sweating

- hunger
- confusion

- weakness
- shaking or feeling jittery

- Allergic (hypersensitivity) reactions. Serious allergic reactions have happened in people who are taking JENTADUETO. Symptoms may include:

- swelling of your face, lips, tongue, throat, and other areas on your skin
- raised, red areas on your skin (hives)

- difficulty with swallowing or breathing
- skin rash, itching, flaking, or peeling

If you have any of these symptoms, stop taking JENTADUETO and call your healthcare provider right away or go to the nearest hospital emergency room.

- Low vitamin B12 (vitamin B12 deficiency). Using metformin for long periods of time may cause a decrease in the amount of vitamin B12 in your blood, especially if you have had low vitamin B12 blood levels before. Your healthcare provider may do blood tests to check your vitamin B12 levels.
- Joint pain. Some people who take linagliptin, one of the medicines in JENTADUETO, may develop joint pain that can be severe. Call your healthcare provider if you have severe joint pain.
- Skin reaction. Some people who take medicines called DPP-4 inhibitors, one of the medicines in JENTADUETO, may develop a skin reaction called bullous pemphigoid that can require treatment in a hospital. Tell your healthcare provider right away if you develop blisters or the breakdown of the outer layer of your skin (erosion). Your healthcare provider may tell you to stop taking JENTADUETO.
- Heart failure. Heart failure means your heart does not pump blood well enough.
  Before you start taking JENTADUETO, tell your healthcare provider if you have ever had heart failure or have problems with your kidneys. Contact your healthcare provider right away if you have any of the following symptoms:
  - increasing shortness of breath or trouble breathing, especially when you lie down
  - swelling or fluid retention, especially in the feet, ankles or legs
  - an unusually fast increase in weight
  - unusual tiredness
  These may be symptoms of heart failure.

The most common side effects of JENTADUETO include:

- stuffy or runny nose and sore throat
- diarrhea

Tell your healthcare provider if you have any side effects that bother you or that do not go away.

These are not all the possible side effects of JENTADUETO. For more information, ask your healthcare provider or pharmacist.

Call your doctor for medical advice about side effects. You may report side effects to FDA at 1-800-FDA-1088.

How should I store JENTADUETO?

- Store JENTADUETO at room temperature between 68°F and 77°F (20°C and 25°C).
- Keep tablets dry.
- Keep JENTADUETO and all medicines out of the reach of children.

General information about the safe and effective use of JENTADUETO.

Medicines are sometimes prescribed for purposes other than those listed in a Medication Guide. Do not use JENTADUETO for a condition for which it was not prescribed. Do not give JENTADUETO to other people, even if they have the same symptoms you have. It may harm them.

You can ask your pharmacist or healthcare provider for information about JENTADUETO that is written for health professionals.

What are the ingredients in JENTADUETO?

Active Ingredients: linagliptin and metformin HCl

Inactive Ingredients: arginine, colloidal silicon dioxide, copovidone, corn starch, hypromellose, magnesium stearate, propylene glycol, talc, titanium dioxide

2.5 mg/500 mg and 2.5 mg/850 mg tablets also contain yellow ferric oxide.

2.5 mg/850 mg and 2.5 mg/1,000 mg tablets also contain red ferric oxide.

Distributed by: Boehringer Ingelheim Pharmaceuticals, Inc. Ridgefield, CT 06877 USA.
Licensed from: Boehringer Ingelheim International GmbH, Ingelheim, Germany.
JENTADUETO is a registered trademark of and used under license from Boehringer Ingelheim International GmbH.
Boehringer Ingelheim Pharmaceuticals, Inc. either owns or uses the Tradjenta®, CARMELINA®, and CAROLINA® trademarks under license.
The other brands listed are trademarks of their respective owners and are not trademarks of Boehringer Ingelheim Pharmaceuticals, Inc.
Copyright © 2023 Boehringer Ingelheim International GmbH
ALL RIGHTS RESERVED

COL9414DF212023

For more information about JENTADUETO, including current prescribing information and Medication Guide, go to www.JENTADUETO.com, scan the code, or call Boehringer Ingelheim Pharmaceuticals, Inc. at 1-800-542-6257.

This Medication Guide has been approved by the U.S. Food and Drug Administration.

Revised: June 2023

PRINCIPAL DISPLAY PANEL - 2.5 mg/850 mg Tablet Bottle Label

NDC 0597-0147-60

DISPENSE THE ACCOMPANYING
MEDICATION GUIDE TO EACH
PATIENT

Jentadueto®
(linagliptin and
metformin
hydrochloride
tablets)

2.5 mg/850 mg*

60 tablets

Rx only

Boehringer
Ingelheim

PRINCIPAL DISPLAY PANEL - 2.5 mg/1,000 mg Tablet Bottle Label

NDC 0597-0148-60

DISPENSE THE ACCOMPANYING
MEDICATION GUIDE TO EACH
PATIENT

Jentadueto®
(linagliptin and
metformin
hydrochloride
tablets)

2.5 mg/1,000 mg*

60 tablets

Rx only

Boehringer
Ingelheim

PRINCIPAL DISPLAY PANEL - 2.5 mg/500 mg Tablet Bottle Label

NDC 0597-0146-60

DISPENSE THE ACCOMPANYING
MEDICATION GUIDE TO EACH
PATIENT

Jentadueto®
(linagliptin and
metformin
hydrochloride
tablets)

2.5 mg/500 mg*

60 tablets

Rx only

Boehringer
Ingelheim